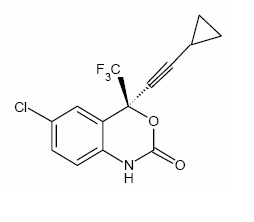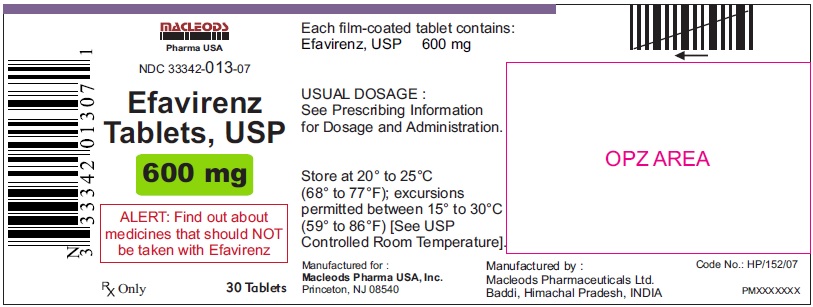 DRUG LABEL: Efavirenz
NDC: 33342-013 | Form: TABLET
Manufacturer: Macleods Pharmaceuticals Limited
Category: prescription | Type: Human Prescription Drug Label
Date: 20240628

ACTIVE INGREDIENTS: EFAVIRENZ 600 mg/1 1
INACTIVE INGREDIENTS: LACTOSE MONOHYDRATE; CROSCARMELLOSE SODIUM; HYDROXYPROPYL CELLULOSE; CELLULOSE, MICROCRYSTALLINE; SODIUM LAURYL SULFATE; MAGNESIUM STEARATE; HYPROMELLOSES; TITANIUM DIOXIDE; POLYETHYLENE GLYCOL 400; FERRIC OXIDE YELLOW

HIGHLIGHTS OF PRESCRIBING INFORMATION

These highlights do not include all the information needed to use EFAVIRENZ safely and effectively. See full prescribing information for EFAVIRENZ TABLETS
EFAVIRENZ tablets, for oral use
Initial U.S. Approval: 1998

1 INDICATIONS & USAGE

Efavirenz is a non-nucleoside reverse transcriptase inhibitor indicated in combination with other antiretroviral agents for the treatment of human immunodeficiency virus type 1 infection in adults and in pediatric patients at least 3 months old and weighing at least 3.5 kg.(1)

2 DOSAGE & ADMINISTRATION

• Efavirenz should be taken orally once daily on an empty stomach, preferably at bedtime. (2)
• Recommended adult dose: 600 mg. (2.2)
• With rifampin, increase efavirenz dose to 800 mg once daily for patients weighing 50 kg or more. (2.2)
• Pediatric dosing is based on weight. (2.3)

3 DOSAGE FORMS & STRENGTHS

•Tablets: 600 mg (3)

4 CONTRAINDICATIONS

•Patients with previously demonstrated hypersensitivity (e.g., Stevens-Johnson syndrome, erythema multiforme, or toxic skin eruptions to any of the components of this product. (4)
•Coadministration of efavirenz with elbasvir/grazoprevir

5 WARNINGS AND PRECAUTIONS

•QTc prolongation: Consider alternatives to efavirenz in patients taking other medications with a known risk of Torsade de Pointes or in patients at higher risk of Torsade de Pointes. (5.2)
•Do not use as a single agent or add on as a sole agent to a failing regimen. Consider potential for cross resistance when choosing other agents. (5.3)

•Not recommended with ATRIPLA, which contains efavirenz, emtricitabine, and tenofovir disoproxil fumarate, unless needed for dose adjustment when coadministered with rifampin. (5.4)
•Serious psychiatric symptoms: Immediate medical evaluation is recommended for serious psychiatric symptoms such as severe depression or suicidal ideation. (5.5,17)
• Nervous system symptoms (NSS): NSS are frequent and usually begin 1-2 days after initiating therapy and resolve in 2-4 weeks. Dosing at bedtime may improve tolerability. NSS are not predictive of onset of psychiatric symptoms. (5.6, 6.1, 17)
•Embryo-Fetal Toxicity: Avoid administration in the first trimester of pregnancy as fetal harm may occur. (5.7, 8.1)
•Hepatotoxicity: Monitor liver function tests before and during treatment in patients with underlying hepatic disease, including hepatitis B or C coinfection, marked transaminase elevations, or who are taking medications associated with liver toxicity. Among reported cases of hepatic failure, a few occurred in patients with no pre-existing hepatic disease. (5.9,6.1, 8.6)
•Rash: Rash usually begins within 1-2 weeks after initiating therapy and resolves within 4 weeks. Discontinue if severe rash develops. (5.8, 6.1, 17)
•Convulsions: Use caution in patients with a history of seizures. (5.10)
•Lipids: Total cholesterol and triglyceride elevations. Monitor before therapy and periodically thereafter. (5.11)
•Immune reconstitution syndrome: May necessitate further evaluation and treatment. (5.12)
•Redistribution/accumulation of body fat: Observed in patients receiving antiretroviral therapy. (5.13,17)

6 ADVERSE REACTIONS

Most common adverse reactions (>5%, moderate-severe) are impaired concentration, abnormal dreams, rash, dizziness, nausea, headache, fatigue, insomnia, and vomiting.(6)
To report SUSPECTED ADVERSE REACTIONS, contact Macleods Pharmaceutical Ltd at 1-888-943-3210 or 1-855-926-3384 or FDA at 1-800-FDA-1088 or www.fda.gov/medwatch.

7 DRUG INTERACTIONS

Coadministration of efavirenz can alter the concentrations of other drugs and other drugs may alter the concentrations of efavirenz. The potential for drug-drug interactions should be considered before and during therapy. (7)

8 USE IN SPECIFIC POPULATIONS

•Lactation: Breastfeeding not recommended. (8.2)
•Females and Males of Reproductive Potential: Pregnancy testing and contraception are recommended. (8.3)
•Hepatic impairment: Efavirenz is not recommended for patients with moderate or severe hepatic impairment. Use caution in patients with mild hepatic impairment. (8.6)
•Pediatric patients: The incidence of rash was higher than in adults. (5.8, 6.2, 8.4)

FULL PRESCRIBING INFORMATION

1 INDICATIONS & USAGE

Efavirenz in combination with other antiretroviral agents is indicated for the treatment of human immunodeficiency virus type 1 (HIV-1) infection in adults and in pediatric patients at least 3 months old and weighing at least 3.5 kg.

2 DOSAGE & ADMINISTRATION

2.1 Hepatic Function

Monitor hepatic function prior to and during treatment with efavirenz [see Warnings and Precautions (5.9)].
Efavirenz is not recommended in patients with moderate or severe hepatic impairment (Child Pugh B or C) [see Warnings and Precautions (5.9) and Use in Specific Populations (8.6)].

2.2 Adults

The recommended dosage of efavirenz is 600 mg orally, once daily, in combination with a protease inhibitor and/or nucleoside analogue reverse transcriptase inhibitors (NRTIs). It is recommended that efavirenz be taken on an empty stomach, preferably at bedtime. The increased efavirenz concentrations observed following administration of efavirenz with food may lead to an increase in frequency of adverse reactions [see Clinical Pharmacology (12.3)]. Dosing at bedtime may improve the tolerability of nervous system symptoms [see Warnings and Precautions (5.6), Adverse Reactions (6.1), and Patient Counseling Information (17)]. Efavirenz capsules or tablets should be swallowed intact with liquid.

Concomitant Antiretroviral Therapy
Efavirenz must be given in combination with other antiretroviral medications [see Indications and Usage (1), Warnings and Precautions (5.3), Drug Interactions (7.1), and Clinical Pharmacology (12.3)].
Dosage Adjustment
If efavirenz is coadministered with voriconazole, the voriconazole maintenance dose should be increased to 400 mg every 12 hours and the efavirenz dose should be decreased to 300 mg once daily using the capsule formulation (one 200 mg and two 50 mg capsules or six 50 mg capsules). Efavirenz tablets must not be broken. [See Drug Interactions (7.1, Table 5) and Clinical Pharmacology (12.3, Tables 7 and 8] .
If efavirenz is coadministered with rifampin to patients weighing 50 kg or more, an increase in the dose of efavirenz to 800 mg once daily is recommended [see Drug Interactions (7.1, Table 5) and Clinical Pharmacology (12.3, Table 8)].

2.3 Pediatric Patients

It is recommended that efavirenz be taken on an empty stomach, preferably at bedtime. Table 1 describes the recommended dose of efavirenz for pediatric patients 3 months of age or older and weighing between 3.5 kg and 40 kg [see Clinical Pharmacology (12.3)]. The recommended dosage of efavirenz for pediatric patients weighing 40 kg or greater is 600 mg once daily. For pediatric patients who cannot swallow capsules, the capsule contents can be administered with a small amount of food or infant formula using the capsule sprinkle method of administration .

Table 1: Efavirenz Dosing in Pediatric Patients
Patient Body Weight | Efavirenz Daily Dose | Number of Capsulesa or Tabletsb and Strength to Administer
3.5 kg to less than 5 kg | 100 mg | two 50 mg capsules
5 kg to less than 7.5 kg | 150 mg | three 50 mg capsule
7.5 kg to less than 15 kg | 200 mg | one 200 mg capsule
15 kg to less than 20 kg | 250 mg | one 200 mg + one 50 mg capsule
20 kg to less than 25 kg | 300 mg | one 200 mg + two 50 mg capsules
25 kg to less than 32.5 kg | 350 mg | one 200 mg + three 50 mg capsules
32.5 kg to less than 40 kg | 400 mg | two 200 mg capsules
at least 40 kg | 600 mg | one 600 mg tablet OR three 200 mg capsules

aCapsules can be administered intact or as sprinkles [see Dosage and Administration (2.4)].

bTablets must not be crushed

3 DOSAGE FORMS & STRENGTHS

• Efavirenz Tablets, USP 600 mg
600-mg tablets are yellow, biconvex, capsule-shaped, film-coated tablets, engraved with "ML 12" on one side and plain on the other side.

4 CONTRAINDICATIONS

• Efavirenz is contraindicated in patients with previously demonstrated clinically significant hypersensitivity (e.g., Stevens-Johnson syndrome, erythema multiforme, or toxic skin eruptions) to any of the components of this product.
• Coadministration of efavirenz with elbasvir and grazoprevir is contraindicated [see Warnings and Precautions (5.1) and Drug Interactions (7.1)].

5 WARNINGS AND PRECAUTIONS

5.1 Drug Interactions

Efavirenz plasma concentrations may be altered by substrates, inhibitors, or inducers of CYP3A. Likewise, efavirenz may alter plasma concentrations of drugs metabolized by CYP3A or CYP2B6. The most prominent effect of efavirenz at steady-state is induction of CYP3A and CYP2B6 [see Dosage and Administration (2.2) and Drug Interactions (7.1)].

5.2 QTc Prolongation

QTc prolongation has been observed with the use of efavirenz [see Drug Interactions (7.3, 7.4) and Clinical Pharmacology (12.2)]. Consider alternatives to efavirenz when coadministered with a drug with a known risk of Torsade de Pointes or when administered to patients at higher risk of Torsade de Pointes.

5.3 Resistance

Efavirenz must not be used as a single agent to treat HIV-1 infection or added on as a sole agent to a failing regimen. Resistant virus emerges rapidly when efavirenz is administered as monotherapy. The choice of new antiretroviral agents to be used in combination with efavirenz should take into consideration the potential for viral cross-resistance.

5.4 Coadministration with Related Products

Coadministration of efavirenz with ATRIPLA (efavirenz 600 mg/emtricitabine 200 mg/tenofovir disoproxil fumarate 300 mg) is not recommended unless needed for dose adjustment (e.g., with rifampin), since efavirenz is one of its active ingredients.

5.5 Psychiatric Symptoms

Serious psychiatric adverse experiences have been reported in patients treated with efavirenz. In controlled trials of 1008 patients treated with regimens containing efavirenz for a mean of 2.1 years and 635 patients treated with control regimens for a mean of 1.5 years, the frequency (regardless of causality) of specific serious psychiatric events among patients who received efavirenz or control regimens, respectively, were severe depression (2.4%, 0.9%), suicidal ideation (0.7%, 0.3%), nonfatal suicide attempts (0.5%, 0), aggressive behavior (0.4%, 0.5%), paranoid reactions (0.4%, 0.3%), and manic reactions (0.2%, 0.3%). When psychiatric symptoms similar to those noted above were combined and evaluated as a group in a multifactorial analysis of data from Study 006, treatment with efavirenz was associated with an increase in the occurrence of these selected psychiatric symptoms. Other factors associated with an increase in the occurrence of these psychiatric symptoms were history of injection drug use, psychiatric history, and receipt of psychiatric medication at study entry; similar associations were observed in both the efavirenz and control treatment groups. In Study 006, onset of new serious psychiatric symptoms occurred throughout the study for both efavirenz-treated and control-treated patients. One percent of efavirenz -treated patients discontinued or interrupted treatment because of one or more of these selected psychiatric symptoms. There have also been occasional postmarketing reports of death by suicide, delusions, and psychosis-like behavior although a causal relationship to the use of efavirenz cannot be determined from these reports. Postmarketing cases of catatonia have also been reported and may be associated with increased efavirenz exposure. Patients with serious psychiatric adverse experiences should seek immediate medical evaluation to assess the possibility that the symptoms may be related to the use of efavirenz, and if so, to determine whether the risks of continued therapy outweigh the benefits [see Adverse Reactions (6.1)].

5.6 Nervous System Symptoms

Fifty-three percent (531/1008) of patients receiving efavirenz in controlled trials reported central nervous system symptoms (any grade, regardless of causality) compared to 25% (156/635) of patients receiving control regimens [see Adverse Reactions (6.1, Table 3)]. These symptoms included, but were not limited to, dizziness (28.1% of the 1008 patients), insomnia (16.3%), impaired concentration (8.3%), somnolence (7.0%), abnormal dreams (6.2%), and hallucinations (1.2%). These symptoms were severe in 2.0% of patients; and 2.1% of patients discontinued therapy as a result. These symptoms usually begin during the first or second day of therapy and generally resolve after the first 2-4 weeks of therapy. After 4 weeks of therapy, the prevalence of nervous system symptoms of at least moderate severity ranged from 5% to 9% in patients treated with regimens containing efavirenz and from 3% to 5% in patients treated with a control regimen. Patients should be informed that these common symptoms were likely to improve with continued therapy and were not predictive of subsequent onset of the less frequent psychiatric symptoms [see Warnings and Precautions (5.5)]. Dosing at bedtime may improve the tolerability of these nervous system symptoms [see Dosage and Administration (2)].
Analysis of long-term data from Study 006 (median follow-up 180 weeks, 102 weeks, and 76 weeks for patients treated with efavirenz + zidovudine + lamivudine, efavirenz + indinavir, and indinavir + zidovudine + lamivudine, respectively) showed that, beyond 24 weeks of therapy, the incidences of new-onset nervous system symptoms among efavirenz-treated patients were generally similar to those in the indinavir-containing control arm.
Late-onset neurotoxicity, including ataxia and encephalopathy (impaired consciousness, confusion, psychomotor slowing, psychosis, delirium), may occur months to years after beginning efavirenz therapy. Some events of late-onset neurotoxicity have occurred in patients with CYP2B6 genetic polymorphisms which are associated with increased efavirenz levels despite standard dosing of efavirenz. Patients presenting with signs and symptoms of serious neurologic adverse experiences should be evaluated promptly to assess the possibility that these events may be related to efavirenz use, and whether discontinuation of efavirenz is warranted.
Patients receiving efavirenz should be alerted to the potential for additive central nervous system effects when efavirenz is used concomitantly with alcohol or psychoactive drugs.
Patients who experience central nervous system symptoms such as dizziness, impaired concentration, and/or drowsiness should avoid potentially hazardous tasks such as driving or operating machinery.

5.7 Embryo-Fetal Toxicity

Efavirenz may cause fetal harm when administered during the first trimester to a pregnant woman. Advise females of reproductive potential who are receiving efavirenz to avoid pregnancy [see Use in Specific Populations (8.1 and 8.3)].

5.8 Rash

In controlled clinical trials, 26% (266/1008) of adult patients treated with 600 mg efavirenz experienced new-onset skin rash compared with 17% (111/635) of those treated in control groups [see Adverse Reactions (6.1)]. Rash associated with blistering, moist desquamation, or ulceration occurred in 0.9% (9/1008) of patients treated with efavirenz. The incidence of Grade 4 rash (e.g., erythema multiforme, Stevens-Johnson syndrome) in adult patients treated with efavirenz in all studies and expanded access was 0.1%. Rashes are usually mild-to-moderate maculopapular skin eruptions that occur within the first 2 weeks of initiating therapy with efavirenz (median time to onset of rash in adults was 11 days) and, in most patients continuing therapy with efavirenz, rash resolves within 1 month (median duration, 16 days). The discontinuation rate for rash in adult clinical trials was 1.7% (17/1008).
Rash was reported in 59 of 182 pediatric patients (32%) treated with efavirenz [see Adverse Reactions (6.2)]. Two pediatric patients experienced Grade 3 rash (confluent rash with fever, generalized rash), and four patients had Grade 4 rash (erythema multiforme). The median time to onset of rash in pediatric patients was 28 days (range 3-1642 days). Prophylaxis with appropriate antihistamines before initiating therapy with efavirenz in pediatric patients should be considered.
Efavirenz can generally be reinitiated in patients interrupting therapy because of rash. Efavirenz should be discontinued in patients developing severe rash associated with blistering, desquamation, mucosal involvement, or fever. Appropriate antihistamines and/or corticosteroids may improve the tolerability and hasten the resolution of rash. For patients who have had a life-threatening cutaneous reaction (e.g., Stevens-Johnson syndrome), alternative therapy should be considered [see Contraindications (4)].

5.9 Hepatotoxicity

Postmarketing cases of hepatitis, including fulminant hepatitis progressing to liver failure requiring transplantation or resulting in death, have been reported in patients treated with efavirenz. Reports have included patients with underlying hepatic disease, including coinfection with hepatitis B or C, and patients without pre-existing hepatic disease or other identifiable risk factors.
Efavirenz is not recommended for patients with moderate or severe hepatic impairment. Careful monitoring is recommended for patients with mild hepatic impairment receiving efavirenz. [see Adverse Reactions (6.1) and Use in Specific Populations (8.6)].
Monitoring of liver enzymes before and during treatment is recommended for all patients [see Dosage and Administration (2.1)]. Consider discontinuing efavirenz in patients with persistent elevations of serum transaminases to greater than five times the upper limit of the normal range.
Discontinue efavirenz if elevation of serum transaminases is accompanied by clinical signs or symptoms of hepatitis or hepatic decompensation.

5.10 Convulsions

Convulsions have been observed in adult and pediatric patients receiving efavirenz, generally in the presence of known medical history of seizures [see Nonclinical Toxicology (13.2)]. Caution should be taken in any patient with a history of seizures. Patients who are receiving concomitant anticonvulsant medications primarily metabolized by the liver, such as phenytoin and phenobarbital, may require periodic monitoring of plasma levels [see Drug Interactions (7.1)].

5.11 Lipid Evaluations

Treatment with efavirenz has resulted in increases in the concentration of total cholesterol and triglycerides [see Adverse Reactions (6.1)]. Cholesterol and triglyceride testing should be performed before initiating efavirenz therapy and at periodic intervals during therapy.

5.12 Immune Reconstitution Syndrome

Immune reconstitution syndrome has been reported in patients treated with combination antiretroviral therapy, including efavirenz. During the initial phase of combination antiretroviral treatment, patients whose immune system responds may develop an inflammatory response to indolent or residual opportunistic infections (such as Mycobacterium avium infection, cytomegalovirus, Pneumocystis jirovecii pneumonia [PCP], or tuberculosis), which may necessitate further evaluation and treatment.
Autoimmune disorders (such as Graves disease, polymyositis, Guillain-Barré syndrome, and autoimmune hepatitis) have also been reported to occur in the setting of immune reconstitution; however, the time to onset is more variable, and can occur many months after initiation of treatment.

5.13 Fat Redistribution

Redistribution/accumulation of body fat including central obesity, dorsocervical fat enlargement (buffalo hump), peripheral wasting, facial wasting, breast enlargement, and "cushingoid appearance" have been observed in patients receiving antiretroviral therapy. The mechanism and long-term consequences of these events are currently unknown. A causal relationship has not been established.

6 ADVERSE REACTIONS

The most significant adverse reactions observed in patients treated with efavirenz are:
•psychiatric symptoms [see Warnings and Precautions (5.5)],
•nervous system symptoms [see Warnings and Precautions (5.6)],
•rash [see Warnings and Precautions (5.8)].
•hepatotoxicity [see Warnings and Precautions (5.9)]

6.1 Clinical Trials Experience

Because clinical studies are conducted under widely varying conditions, the adverse reaction rates reported cannot be directly compared to rates in other clinical studies and may not reflect the rates observed in clinical practice.
Adverse Reactions in Adults.
The most common (>5% in either efavirenz treatment group) adverse reactions of at least moderate severity among patients in Study 006 treated with efavirenz in combination with zidovudine/lamivudine or indinavir were rash, dizziness, nausea, headache, fatigue, insomnia, and vomiting
Selected clinical adverse reactions of moderate or severe intensity observed in ≥2% of efavirenz-treated patients in two controlled clinical trials are presented in Table 2

Table 2: Selected Treatment-Emergenta Adverse Reactions of Moderate or Severe Intensity Reported in ≥2% of EFAVIRENZ TABLETS-Treated Patients in Studies 006 and ACTG 364
 | Study 006 LAM-, NNRTI-, and Protease Inhibitor-Naive Patients |  |  | Study ACTG 364 NRTI-experienced, NNRTI- and Protease Inhibitor-Naive Patients
Adverse Reactions | Efavirenzb + ZDV/LAM (n=412) | Efavirenzb+ Indinavir (n=415) | Indinavir + ZDV/LAM (n=401) | Efavirenzb + Nelfinavir + NRTIs (n=64) | Efavirenzb + NRTIs (n=65) | Nelfinavir + NRTIs (n=66)
Adverse Reactions | 180 weeksc | 102 weeksc | 76 weeksc | 71.1 weeksc | 70.9 weeksc | 62.7 weeksc
Psychiatric
Body as a Whole
Fatigue | 8% | 5% | 9% | 0 | 2% | 3%
Pain | 1% | 2% | 8% | 13% | 6% | 17%
Central and Peripheral Nervous System
Dizziness | 9% | 9% | 2% | 2% | 6% | 6%
Headache | 8% | 5% | 3% | 5% | 2% | 3%
Insomnia | 7% | 7% | 2% | 0 | 0 | 2%
Concentration impaired | 5% | 3% | <1% | 0 | 0 | 0
Abnormal dreams | 3% | 1% | 0 | — | — | —
Somnolence | 2% | 2% | <1% | 0 | 0 | 0
Anorexia | 1% | <1% | <1% | 0 | 2% | 2%
Gastrointestinal
Nausea | 10% | 6% | 24% | 3% | 2% | 2%
Vomiting | 6% | 3% | 14% | — | — | —
Diarrhea | 3% | 5% | 6% | 14% | 3% | 9%
Dyspepsia | 4% | 4% | 6% | 0 | 0 | 2%
Abdominal pain | 2% | 2% | 5% | 3% | 3% | 3%
Anxiety | 2% | 4% | <1% | — | — | —
Depression | 5% | 4% | <1% | 3% | 0 | 5%
Nervousness | 2% | 2% | 0 | 2% | 0 | 2%
Skin & Appendages
Rashd | 11% | 16% | 5% | 9% | 5% | 9%
Pruritis | <1% | 1% | 1% | 9% | 5% | 9%
a Includes adverse events at least possibly related to study drug or of unknown relationship for Study 006. Includes all adverse events regardless of relationship to study drug for Study ACTG 364.
b Efavirenz tablets provided as 600 mg once daily.
c Median duration of treatment.
d Includes erythema multiforme, rash, rash erythematous, rash follicular, rash maculopapular, rash petechial, rash pustular, and urticaria for Study 006 and macules, papules, rash, erythema, redness, inflammation, allergic rash, urticaria, welts, hives, itchy, and pruritus for ACTG 364.
— = Not Specified.
ZDV = zidovudine, LAM=lamivudine.

Pancreatitis has been reported, although a causal relationship with efavirenz has not been established. Asymptomatic increases in serum amylase levels were observed in a significantly higher number of patients treated with efavirenz 600 mg than in control patients (see Laboratory Abnormalities).
Nervous System Symptoms
For 1008 patients treated with regimens containing efavirenz and 635 patients treated with a control regimen in controlled trials, Table 3 lists the frequency of symptoms of different degrees of severity and gives the discontinuation rates for one or more of the following nervous system symptoms: dizziness, insomnia, impaired concentration, somnolence, abnormal dreaming, euphoria, confusion, agitation, amnesia, hallucinations, stupor, abnormal thinking, and depersonalization [see Warnings and Precautions (5.6)]. The frequencies of specific central and peripheral nervous system symptoms are provided in Table 2

Table 3: Percent of Patients with One or More Selected Nervous System Symptoms a,b
Percent of Patients with: | EFAVIRENZ TABLETS 600 mg Once Daily (n=1008) | Control Groups (n=635)
Percent of Patients with: | % | %
Symptoms of any severity | 52.7 | 24.6
Mild symptomsc | 33.3 | 15.6
Moderate symptomsd | 17.4 | 7.7
Severe symptomse | 2.0 | 1.3
Treatment discontinuation as a result of symptoms | 2.1 | 1.1

a Includes events reported regardless of causality.
b Data from Study 006 and three Phase 2/3 studies.
c "Mild" = Symptoms which do not interfere with patient’s daily activities.
d "Moderate" = Symptoms which may interfere with daily activities.
e "Severe" = Events which interrupt patient’s usual daily activities.

Psychiatric Symptoms
Serious psychiatric adverse experiences have been reported in patients treated with efavirenz tablets. In controlled trials, psychiatric symptoms observed at a frequency of greater than 2% among patients treated with efavirenz or control regimens, respectively, were depression (19%, 16%), anxiety (13%, 9%), and nervousness (7%, 2%).
Rash
In controlled clinical trials, the frequency of rash (all grades, regardless of causality) was 26% for 1008 adults treated with regimens containing efavirenz and 17% for 635 adults treated with a control regimen. Most reports of rash were mild or moderate in severity. The frequency of Grade 3 rash was 0.8% for efavirenz -treated patients and 0.3% for control groups, and the frequency of Grade 4 rash was 0.1% for efavirenz and 0 for control groups. The discontinuation rates as a result of rash were 1.7% for efavirenz -treated patients and 0.3% for control groups [see Warnings and Precautions (5.8)].
Experience with efavirenz in patients who discontinued other antiretroviral agents of the NNRTI class is limited. Nineteen patients who discontinued nevirapine because of rash have been treated with efavirenz. Nine of these patients developed mild-to-moderate rash while receiving therapy with efavirenz, and two of these patients discontinued because of rash.
Laboratory Abnormalities

Selected Grade 3-4 laboratory abnormalities reported in greater than 2% of efavirenz tablets-treated patients in two clinical trials are presented in Table 4.

Table 4: Selected Grade 3-4 Laboratory Abnormalities Reported in≥2% of EFAVIRENZ TABLETS-Treated Patients in Studies 006 and ACTG 364
 |  | Study 006 LAM-, NNRTI-, and Protease Inhibitor-Naive Patients |  |  |  | Study ACTG 364 NRTI-experienced, NNRTI- and Protease Inhibitor-Naive Patients
Variable | Limit | EFAVI RENZa+ ZDV/ LAM (n=412) |  | EFAVI RENZa + Indinavir (n=415) | Indina vir + ZDV/ LAM (n=401) | EFAVI RENZa + Nelfinavir + NRTIs (n=64) | EFAVI RENZa + NRTIs (n=65) | Nelfi navir + NRTIs (n=66)
Variable | Limit | 180 weeksb |  | 102 weeksb | 76 weeksb | 71.1 weeksb | 70.9 weeksb | 62.7 weeksb
Chemistry
ALT | >5 x ULN | 5% |  | 8% | 5% | 2% | 6% |  | 3%
AST | >5 x ULN | 5% |  | 6% | 5% | 6% | 8% |  | 8%
GGTc | >5 x ULN | 8% |  | 7% | 3% | 5% | 0 |  | 5%
Amylase | >2 x ULN | 4% |  | 4% | 1% | 0 | 6% |  | 2%
Glucose | >250 mg/dL | 3% |  | 3% | 3% | 5% | 2% |  | 3%
Triglyce ridesd | ≥751 mg/dL | 9% |  | 6% | 6% | 11% | 8% |  | 17%
Hematology
Neutrophils | <750/mm^3 |  | 10% | 3% | 5% | 2% | 3% |  | 2%
a Efairenz tablets provided as 600 mg once daily.
b Median duration of treatment.
c Isolated elevations of GGT in patients receiving efavirenz may reflect enzyme induction not associated with liver toxicity.
d Nonfasting.
ZDV = zidovudine, LAM = lamivudine, ULN = Upper limit of normal, ALT = alanine aminotransferase,
AST = aspartate aminotransferase, GGT = gamma-glutamyltransferase

Patients Coinfected with Hepatitis B or C
Liver function tests should be monitored in patients with a history of hepatitis B and/or C. In the long-term data set from Study 006, 137 patients treated with efavirenz-containing regimens (median duration of therapy, 68 weeks) and 84 treated with a control regimen (median duration, 56 weeks) were seropositive at screening for hepatitis B (surface antigen positive) and/or C (hepatitis C antibody positive). Among these coinfected patients, elevations in AST to greater than five times ULN developed in 13% of patients in the efavirenz arms and 7% of those in the control arm, and elevations in ALT to greater than five times ULN developed in 20% of patients in the efavirenz arms and 7% of patients in the control arm. Among coinfected patients, 3% of those treated with efavirenz -containing regimens and 2% in the control arm discontinued from the study because of liver or biliary system disorders [see Warnings and Precautions (5.9)].
Lipids
Increases from baseline in total cholesterol of 10-20% have been observed in some uninfected volunteers receiving efavirenz. In patients treated with efavirenz + zidovudine + lamivudine, increases from baseline in nonfasting total cholesterol and HDL of approximately 20% and 25%, respectively, were observed. In patients treated with efavirenz + indinavir, increases from baseline in nonfasting cholesterol and HDL of approximately 40% and 35%, respectively, were observed. Nonfasting total cholesterol levels ≥240 mg/dL and ≥300 mg/dL were reported in 34% and 9%, respectively, of patients treated with efavirenz + zidovudine + lamivudine; 54% and 20%, respectively, of patients treated with efavirenz + indinavir; and 28% and 4%, respectively, of patients treated with indinavir + zidovudine + lamivudine. The effects of efavirenz on triglycerides and LDL in this study were not well characterized since samples were taken from nonfasting patients. The clinical significance of these findings is unknown [see Warnings and Precautions (5.11)].
Adverse Reactions in Pediatric Patients
Because clinical studies are conducted under widely varying conditions, the adverse reaction rates reported cannot be directly compared to rates in other clinical studies and may not reflect the rates observed in clinical practice.
Assessment of adverse reactions is based on three clinical trials in 182 HIV-1 infected pediatric patients (3 months to 21 years of age) who received efavirenz in combination with other antiretroviral agents for a median of 123 weeks. The adverse reactions observed in the three trials were similar to those observed in clinical trials in adults except that rash was more common in pediatric patients (32% for all grades regardless of causality) and more often of higher grade (ie, more severe). Two (1.1%) pediatric patients experienced Grade 3 rash (confluent rash with fever, generalized rash), and four (2.2%) pediatric patients had Grade 4 rash (all erythema multiforme). Five pediatric patients (2.7%) discontinued from the study because of rash [see Warnings and Precautions (5.8)].

6.2 Postmarketing Experience

The following adverse reactions have been identified during postapproval use of efavirenz tablets. Because these reactions are reported voluntarily from a population of unknown size, it is not always possible to reliably estimate their frequency or establish a causal relationship to drug exposure.
Body as a Whole: allergic reactions, asthenia, redistribution/accumulation of body fat [see Warnings and Precautions (5.13)]
Central and Peripheral Nervous System: abnormal coordination, ataxia, encephalopathy, cerebellar coordination and balance disturbances, convulsions, hypoesthesia, paresthesia, neuropathy, tremor,vertigo
Endocrine: gynecomastia
Gastrointestinal: constipation, malabsorption
Cardiovascular: flushing, palpitations
Liver and Biliary System: hepatic enzyme increase, hepatic failure, hepatitis
Metabolic and Nutritional: hypercholesterolemia, hypertriglyceridemia
Musculoskeletal: arthralgia, myalgia, myopathy
Psychiatric: aggressive reactions, agitation, delusions, emotional lability, mania, neurosis, paranoia, psychosis, suicide, catatonia
Respiratory: dyspnea
Skin and Appendages: erythema multiforme, photoallergic dermatitis, Stevens-Johnson syndrome
Special Senses: abnormal vision, tinnitus

7 DRUG INTERACTIONS

7.1 Potential for efavirenz to Affect other Drugs

Efavirenz has been shown in vivo to induce CYP3A and CYP2B6. Other compounds that are substrates of CYP3A or CYP2B6 may have decreased plasma concentrations when coadministered with efavirenz

7.2 Potential for Other Drugs to Affect efavirenz

Drugs that induce CYP3A activity (e.g., phenobarbital, rifampin, rifabutin) would be expected to increase the clearance of efavirenz resulting in lowered plasma concentrations [see Dosage and Administration (2.2)].

7.3 QT Prolonging Drugs

There is limited information available on the potential for a pharmacodynamic interaction between efavirenz and drugs that prolong the QTc interval. QTc prolongation has been observed with the use of efavirenz [see Clinical Pharmacology (12.2)]. Consider alternatives to efavirenz when coadministered with a drug with a known risk of Torsade de Pointes.

7.4 Established and Other Potentially Significant Drug Interactions

Drug interactions with efavirenz are summarized in Table 5. For pharmacokinetics data, [see Clinical Pharmacology (12.3)] Tables 7 and 8. This table includes potentially significant interactions, but is not all inclusive

Table 5: Established and Other Potentially Significant Drug Interactions: Alteration in Dose or Regimen May Be Recommended Based on Drug Interaction Studies or Predicted Interaction
Concomitant Drug Class: Drug Name | Effect | Clinical Comment
HIV antiviral agents
Protease inhibitor: Fosamprenavir calcium | ↓ amprenavir | Fosamprenavir (unboosted): Appropriate doses of the combinations with respect to safety and efficacy have not been established. Fosamprenavir/ritonavir: An additional 100 mg/day (300 mg total) of ritonavir is recommended when efavirenz tablets are administered with fosamprenavir/ritonavir once daily. No change in the ritonavir dose is required when efavirenz tablets are administered with fosamprenavir plus ritonavir twice daily.
Protease inhibitor: Atazanavir | ↓ atazanavir* | Treatment –naïve patients: When co-administered with efavirenz tablets , the recommended dose of atazanavir is 400 mg with ritonavir 100 mg (together once daily with food) and efavirenz tablets 600 mg (once daily on an empty stomach, preferably at bedtime). Treatment-experienced patients: Co-administration of efavirenz tablets and atazanavir is not recommended.
Protease inhibitor: Indinavir | ↓ indinavir* | The optimal dose of indinavir, when given in combination with efavirenz tablets are not known. Increasing the indinavir dose to 1000 mg every 8 hours does not compensate for the increased indinavir metabolism due to efavirenz .
Protease inhibitor: Lopinavir/ritonavir | ↓ lopinavir* | Lopinavir/ritonavir once daily dosing is not recommended when co-administered with efavirenz. The dose of lopinavir/ritonavir must be increased when co-administered with efavirenz. See the lopinavir/ritonavir prescribing information for dose adjustments of lopinavir/ritonavir when co-administered with efavirenz in adult and pediatric patients.
Protease inhibitor: Ritonavir | ↑ ritonavir* ↑ efavirenz* | Monitor for elevation of liver enzymes and for adverse clinical experiences (e.g., dizziness, nausea, paresthesia) when efavirenz is co-administered with ritonavir.
Protease inhibitor: Saquinavir | ↓ saquinavir* | Appropriate doses of the combination of efavirenz and saquinavir/ritonavir with respect to safety and efficacy have not been established.
NNRTI: Other NNRTIs | ↑ or ↓ efavirenz and/ or NNRTI | Combining two NNRTIs has not been shown to be beneficial. efavirenz should not be coadministered with other NNRTIs.
CCR5 co-receptor antagonist: Maraviroc | ↓ maraviroc* | Refer to the full prescribing information for maraviroc for guidance on co-administration with efavirenz.
Hepatitis C antiviral agents
Boceprevir | ↓ boceprevir* | Concomitant administration of boceprevir with efavirenz is not recommended because it may result in loss of therapeutic effect of boceprevir
Elbasvir/Grazoprevir | ↓ elbasvir ↓ grazoprevir | Co-administration o efavirenz with elbasvir/grazoprevir is contraindicated [see Contraindications (4)] because it may lead to loss of virologic response to elbasvir/grazoprevir.
Pibrentasvir/Glecaprevir | ↓ pibrentasvir | Co-administration of efavirenz is not recommended because it may lead to reduced therapeutic effect of pibrentasvir/glecaprevir
Simeprevir | ↓simeprevir* ↔efavirenz* | Concomitant administration of simeprevir with efavirenz is not recommended because it may result in loss oftherapeutic effect of simeprevir.
Velpatasvir/ Sofosbuvir | ↓ velpatasvir | Co-administration of efavirenz and sofosbuvir/velpatasvir is not recommended because it may result in loss of therapeutic effect of sofosbuvir/velpatasvir
Velpatasvir /Sofosbuvir/Voxilaprevir | ↓ velpatasvir ↓ voxilaprevir | Co-administration of efavirenz and sofosbuvir/velpatasvir/voxilaprevir is not recommended because it may result in loss of therapeutic effect of sofosbuvir/velpatasvir/voxilaprevir.
Other agents
Anticoagulant: Warfarin | ↑ or ↓ warfarin | Monitor INR and adjust warfarin dosage if necessary.
Anticonvulsants: Carbamazepine | ↓ carbamazepine* ↓ efavirenz* | There are insufficient data to make a dose recommendation for efavirenz. Alternative anticonvulsant treatment should be used.
Phenytoin Phenobarbital | ↓ anticonvulsant ↓ efavirenz | Potential for reduction in anticonvulsant and/or efavirenz plasma levels; periodic monitoring of anticonvulsant plasma levels should be conducted.
Antidepressant: Bupropion Sertraline | ↓bupropion* ↓ sertraline* | Increases in bupropion dosage should be guided by clinical response. Bupropion dose should not exceed the maximum recommended dose. Increases in sertraline dosage should be guided by clinical response.
Antifungals: Voriconazole | ↓ voriconazole* ↑ efavirenz* | Efavirenz and voriconazole should not be co-administered at standard doses. When voriconazole is co-administered with efavirenz, voriconazole maintenance dose should be increased to 400 mg every 12 hours and efavirenz dose should be decreased to 300 mg once daily using the capsule formulation. Efavirenz tablets must not be broken. [See Dosage and Administration (2.2) and Clinical Pharmacology (12.3, Tables 7 and 8).]
Itraconazole | ↓ itraconazole* ↓ hydroxyitraconazole* | Since no dose recommendation for itraconazole can be made, alternative antifungal treatment should be considered.
Ketoconazole | ↓ ketoconazole | Drug interaction studies with efavirenz and ketoconazole have not been conducted. efavirenz has the potential to decrease plasma concentrations of ketoconazole.
Posaconazole | ↓ posaconazole* | Avoid concomitant use unless the benefit outweighs the risks.
Anthelmintic: Praziquantel | ↓ praziquantel | Co-administration with efavirenz is not recommended due to significant decrease in plasma concentrations of praziquantel, with risk of treatment failure due to increased hepatic metabolism by efavirenz.
Anti-infective: Clarithromycin | ↓ clarithromycin* ↑ 14-OH metabolite* | Consider alternatives to macrolide antibiotics because of the risk of QT interval prolongation.
Antimycobacterial: Rifabutin | ↓ rifabutin* | Increase daily dose of rifabutin by 50%. Consider doubling the rifabutin dose in regimens where rifabutin is given 2 or 3 times a week.
Rifampin | ↓ efavirenz* | Increase efavirenz to 800 mg once daily when co-administered with rifampin to patients weighing 50 kg or more.
Antimalarials: Artemether/ lumefantrine | ↓ artemether* ↓ dihydroartemisinin* ↓ lumefantrine* | Consider alternatives to artemether/lumefantrine because of the risk of QT interval prolongation.
Atovaquone/ proguanil | ↓ atovaquone ↓ proguanil | Concomitant administration is not recommended.
Calcium channel blockers: Diltiazem | ↓ diltiazem* ↓ desacetyl diltiazem* ↓ N-monodesmethyl diltiazem* | Diltiazem dose adjustments should be guided by clinical response (refer to the complete prescribing information for diltiazem). No dose adjustment of efavirenz is necessary when administered with diltiazem.
Others (e.g., felodipine, nicardipine, nifedipine, verapamil) | ↓ calcium channel blocker | When co-administered with efavirenz, dosage adjustment of calcium channels blocker may be needed and should be guided by clinical response (refer to the full prescribing information for the calcium channel blocker).
HMG-CoA reductase inhibitors: Atorvastatin Pravastatin Simvastatin | ↓ atorvastatin* ↓ pravastatin* ↓ simvastatin* | Plasma concentrations of atorvastatin, pravastatin, and simvastatin decreased. Consult the complete prescribing information for the HMG-CoA reductase inhibitor for guidance on individualizing the dose.
Hormonal contraceptives: Oral Ethinyl estradiol/ Norgestimate Implant Etonogestrel | ↓ active metabolites of Norgestimate* ↓ Etonogestrel | A reliable method of barrier contraception should be used in addition to hormonal contraceptives. A reliable method of barrier contraception should be used in addition to hormonal contraceptives. Decreased exposure of etonogestrel may be expected. There have been post marketing reports of contraceptive failure with etonogestrel in efavirenz-exposed patients.
Immunosuppressants: Cyclosporine, tacrolimus, sirolimus, and others metabolized by CYP3A | ↓ immunosuppressant | Dose adjustments of the immunosuppressant may be required. Close monitoring of immunosuppressant concentrations for at least 2 weeks (until stable concentrations are reached) is recommended when starting metabolized by or stopping treatment with efavirenz.
Narcotic analgesic: Methadone | ↓ methadone* | Monitor for signs of methadone withdrawal and increase methadone dose if required to alleviate withdrawal symptoms.
* The interaction between efavirenz and the drug was evaluated in a clinical study. All other drug interactions shown are predicted. This table is not all-inclusive.

7.5 Drugs Without Clinically Significant Interactions with Efavirenz

No dosage adjustment is recommended when efavirenz is given with the following: aluminum/magnesium hydroxide antacids, azithromycin, cetirizine, famotidine, fluconazole, lorazepam, nelfinavir, nucleoside reverse transcriptase inhibitors (abacavir, emtricitabine, lamivudine, stavudine, tenofovir disoproxil fumarate, zidovudine), paroxetine, and raltegravir.

7.6 Cannabinoid Test Interaction

Efavirenz does not bind to cannabinoid receptors. False-positive urine cannabinoid test results have been reported with some screening assays in uninfected and HIV-infected subjects receiving efavirenz. Confirmation of positive screening tests for cannabinoids by a more specific method is recommended.

8 USE IN SPECIFIC POPULATIONS

8.1 Pregnancy

Pregnancy Exposure Registry
There is a pregnancy exposure registry that monitors pregnancy outcomes in women exposed to efavirenz during pregnancy. Physicians are encouraged to register patients by calling the Antiretroviral Pregnancy Registry at 1-800-258-4263.
Risk Summary
There are retrospective case reports of neural tube defects in infants whose mothers were exposed to efavirenz-containing regimens in the first trimester of pregnancy. Prospective pregnancy data from the Antiretroviral Pregnancy Registry are not sufficient to adequately assess this risk. Available data from the Antiretroviral Pregnancy Registry show no difference in the risk of overall major birth defects compared to the background rate for major birth defects of 2.7% in the U.S. reference population of the Metropolitan Atlanta Congenital Defects Program(MACDP). Although a causal relationship has not been established between exposure to efavirenz in the first trimester and neural tube defects, similar malformations have been observed in studies conducted in monkeys at doses similar to the human dose. In addition, fetal and embryonic toxicities occurred in rats, at a dose ten times less than the human exposure at recommended clinical dose. Because of the potential risk of neural tube defects, efavirenz should not be used in the first trimester of pregnancy. Advise pregnant women of the potential risk to a fetus.
Data
Human Data
There are retrospective postmarketing reports of findings consistent with neural tube defects, including meningomyelocele, all in infants of mothers exposed to efavirenz-containing regimens in the first trimester.
Based on prospective reports from the Antiretroviral Pregnancy Registry (APR) of approximately 1000 live births following exposure to efavirenz-containing regimens (including over 800 live births exposed in the first trimester), there was no difference between efavirenz and overall birth defects compared with the background birth defect rate of 2.7% in the U.S. reference population of the Metropolitan Atlanta Congenital Defects Program. As of the interim APR report issued December 2014, the prevalence of birth defects following first-trimester exposure was 2.3% (95% CI: 1.4%-3.6%). One of these prospectively reported defects with first-trimester exposure was a neural tube defect. A single case of anophthalmia with first-trimester exposure to efavirenz has also been prospectively reported. This case also included severe oblique facial clefts and amniotic banding, which have a known association with anophthalmia.
Animal Data
Effects of efavirenz on embryo-fetal development have been studied in three nonclinical species (cynomolgus monkeys, rats, and rabbits). In monkeys, efavirenz 60 mg/kg/day was administered to pregnant females throughout pregnancy (gestation days 20 through 150). The maternalsystemic drug exposures (AUC) were 1.3 times the exposure in humans at the recommended clinical dose (600 mg/day), with fetal umbilical venous drug concentrations approximately
0.7 times the maternal values. Three of 20 fetuses/infants had one or more malformations; there were no malformed fetuses or infants from placebo-treated mothers. The malformations that occurred in these three monkey fetuses included anencephaly and unilateral anophthalmia in one fetus, microphthalmia in a second, and cleft palate in the third. There was no NOAEL (no observable adverse effect level) established for this study because only one dosage was evaluated. In rats, efavirenz was administered either during organogenesis (gestation days 7 to 18) or from gestation day 7 through lactation day 21 at 50, 100, or 200 mg/kg/day. Administration of 200 mg/kg/day in rats was associated with increase in the incidence of early resorptions; and doses 100 mg/kg/day and greater were associated with early neonatal mortality. The AUC at the NOAEL (50 mg/kg/day) in this rat study was 0.1 times that in humans at the recommended clinical dose. Drug concentrations in the milk on lactation day 10 were approximately 8 times higher than those in maternal plasma. In pregnant rabbits, efavirenz was neither embryo lethal nor teratogenic when administered at doses of 25, 50, and 75 mg/kg/day over the period of organogenesis (gestation days 6 through 18). The AUC at the NOAEL (75 mg/kg/day) in rabbits was 0.4 times that in humans at the recommended clinical dose.

8.2 Lactation

Risk Summary
The Centers for Disease Control and Prevention recommend that HIV-infected mothers not breastfeed their infants to avoid risking postnatal transmission of HIV. Because of the potential for HIV transmission in breastfed infants, advise women not to breastfeed.

8.3 Females and Males of Reproductive Potential

Because of potential teratogenic effects, pregnancy should be avoided in women receiving efavirenz [see Use in Specific Populations (8.1)].
Pregnancy Testing
Females of reproductive potential should undergo pregnancy testing before initiation of efavirenz.
Contraception
Females of reproductive potential should use effective contraception during treatment with efavirenz and for 12 weeks after discontinuing efavirenz due to the long half-life of efavirenz. Barrier contraception should always be used in combination with other methods of contraception. Hormonal methods that contain progesterone may have decreased effectiveness [see Drug Interactions (7.1)].

8.4 Pediatric Use

The safety, pharmacokinetic profile, and virologic and immunologic responses of efavirenz were evaluated in antiretroviral-naive and -experienced HIV-1 infected pediatric patients 3 months to 21 years of age in three open-label clinical trials [see Adverse Reactions (6.2),Clinical Pharmacology (12.3), and Clinical Studies (14.2)]. The type and frequency of adverse reactions in these trials were generally similar to those of adult patients with the exception of a higher frequency of rash, including a higher frequency of Grade 3 or 4 rash, in pediatric patients compared to adults [see Warnings and Precautions (5.8) and Adverse Reactions (6.2)].
Use of efavirenz in patients younger than 3 months of age OR less than 3.5 kg body weight is not recommended because the safety, pharmacokinetics, and antiviral activity of efavirenz have not been evaluated in this age group and there is a risk of developing HIV resistance if efavirenz is underdosed. See Dosage and Administration (2.2) for dosing recommendations for pediatric patients.

8.5 Geriatric Use

Clinical studies of efavirenz did not include sufficient numbers of subjects aged 65 years and over to determine whether they respond differently from younger subjects. In general, dose selection for an elderly patient should be cautious, reflecting the greater frequency of decreased hepatic, renal, or cardiac function and of concomitant disease or other therapy.

8.6 Hepatic Impairment

Efavirenz is not recommended for patients with moderate or severe hepatic impairment because there are insufficient data to determine whether dose adjustment is necessary. Patients with mild hepatic impairment may be treated with efavirenz without any adjustment in dose. Because of the extensive cytochrome P450-mediated metabolism of efavirenz and limited clinical experience in patients with hepatic impairment, caution should be exercised in administering Efavirenz to these patients [see Warnings and Precautions (5.9) and Clinical Pharmacology (12.3)].

10 OVERDOSAGE

Some patients accidentally taking 600 mg twice daily have reported increased nervous system symptoms. One patient experienced involuntary muscle contractions.
Treatment of overdose with efavirenz should consist of general supportive measures, including monitoring of vital signs and observation of the patient's clinical status. Administration of activated charcoal may be used to aid removal of unabsorbed drug. There is no specific antidote for overdose with efavirenz. Since efavirenz is highly protein bound, dialysis is unlikely to significantly remove the drug from blood.

11 DESCRIPTION

Efavirenz, USP is an HIV-1 specific, non-nucleoside, reverse transcriptase inhibitor (NNRTI). Efavirenz is chemically described as(S)-6-chloro-4-(cyclopropylethynyl)-1,4-dihydro4(trifluoromethyl)-2H-3,1-benzoxazin-2-one. Its empirical formula is C14H9ClF3NO2 and its structural formula is:
Efavirenz,USP is a white to slightly pink crystalline powder with a molecular mass of 315.68. It is practically insoluble in water (<10 microgram/mL).

Tablets: Efavirenz USP is available as film-coated tablets for oral administration containing 600 mg of efavirenz and the following inactive ingredients: croscarmellose sodium, hydroxypropyl cellulose, lactose monohydrate, magnesium stearate, microcrystalline cellulose, and sodium lauryl sulfate. The film coating contains Opadry Yellow,consisting of hydroxypropylmethyl cellulose, titanium dioxide, polyethylene glycol and iron oxide yellow.

12 CLINICAL PHARMACOLOGY

12.1 Mechanism of Action

Efavirenz is an antiviral drug [see Microbiology (12.4)].

12.2 Pharmacodynamics

Cardiac Electrophysiology
The effect of efavirenz on the QTc interval was evaluated in an open-label, positive and placebo controlled, fixed single sequence 3-period, 3-treatment crossover QT study in 58 healthy subjects enriched for CYP2B6 polymorphisms. The mean Cmax of efavirenz in subjects with CYP2B6 *6/*6 genotype following the administration of 600 mg daily dose for 14 days was 2.25-fold the mean Cmax observed in subjects with CYP2B6 *1/*1 genotype. A positive relationship between efavirenz concentration and QTc prolongation was observed. Based on the concentration-QTc relationship, the mean QTc prolongation and its upper bound 90% confidence interval are 8.7 ms and 11.3 ms in subjects with CYP2B6*6/*6 genotype following the administration of 600 mg daily dose for 14 days [see Warnings and Precautions (5.2)].

12.3 Pharmacokinetics

Absorption
Peak efavirenz plasma concentrations of 1.6-9.1 μM were attained by 5 hours following single oral doses of 100 mg to 1600 mg administered to uninfected volunteers. Dose-related increases in Cmax and AUC were seen for doses up to 1600 mg; the increases were less than proportional suggesting diminished absorption at higher doses.
In HIV-1-infected patients at steady state, mean Cmax, mean Cmin, and mean AUC were dose proportional following 200 mg, 400 mg, and 600 mg daily doses. Time-to-peak plasma concentrations were approximately 3-5 hours and steady-state plasma concentrations were reached in 6-10 days. In 35 patients receiving efavirenz 600 mg once daily, steady-state Cmax was 12.9 ± 3.7 μM (mean ± SD), steady-state Cmin was 5.6 ± 3.2 μM, and AUC was 184 ± 73 μMh.
Effect of Food on Oral Absorption:
Tablets: Administration of a single 600 mg efavirenz tablet with a high-fat/high-caloric meal (approximately 1000 kcal, 500-600 kcal from fat) was associated with a 28% increase in mean AUC∞ of efavirenz and a 79% increase in mean Cmax of efavirenz relative to the exposures achieved under fasted conditions. [see Dosage and Administration (2) and Patient Counseling Information (17)].
Distribution
Efavirenz is highly bound (approximately 99.5-99.75%) to human plasma proteins, predominantly albumin. In HIV-1 infected patients (n=9) who received efavirenz 200 to 600 mg once daily for at least one month, cerebrospinal fluid concentrations ranged from 0.26 to 1.19% (mean 0.69%) of the corresponding plasma concentration. This proportion is approximately 3-fold higher than the non-protein-bound (free) fraction of efavirenz in plasma.
Metabolism
Studies in humans and in vitro studies using human liver microsomes have demonstrated that efavirenz is principally metabolized by the cytochrome P450 system to hydroxylated metabolites with subsequent glucuronidation of these hydroxylated metabolites. These metabolites are essentially inactive against HIV-1. The in vitro studies suggest that CYP3A and CYP2B6 are the major isozymes responsible for efavirenz metabolism.
Efavirenz has been shown to induce CYP enzymes, resulting in the induction of its own metabolism. Multiple doses of 200-400 mg per day for 10 days resulted in a lower than predicted extent of accumulation (22-42% lower) and a shorter terminal half-life of 40-55 hours (single dose half-life 52-76 hours).
Elimination
Efavirenz has a terminal half-life of 52-76 hours after single doses and 40-55 hours after multiple doses. A one-month mass balance/excretion study was conducted using 400 mg per day with a 14C-labeled dose administered on Day 8. Approximately 14-34% of the radiolabel was recovered in the urine and 16-61% was recovered in the feces. Nearly all of the urinary excretion of the radiolabeled drug was in the form of metabolites. Efavirenz accounted for the majority of the total radioactivity measured in feces.
Special Populations
Pediatric: The pharmacokinetic parameters for efavirenz at steady state in pediatric patients were predicted by a population pharmacokinetic model and are summarized in Table 6 by weight ranges that correspond to the recommended doses.

Table 6: | Predicted Steady-State Pharmacokinetics of Recommended Doses of Efavirenz (Capsules/Capsule Sprinkles) in HIV-Infected Pediatric Patients
Body Weight | Dose | Mean AUC(0-24) μM·h | Mean Cmax μg/mL | Mean Cmin μg/mL
3.5-5 kg | 100 mg | 220.52 | 5.81 | 2.43
5-7.5 kg | 150 mg | 262.62 | 7.07 | 2.71
7.5-10 kg | 200 mg | 284.28 | 7.75 | 2.87
10-15 kg | 200 mg | 238.14 | 6.54 | 2.32
15-20 kg | 250 mg | 233.98 | 6.47 | 2.3
20-25 kg | 300 mg | 257.56 | 7.04 | 2.55
25-32.5 kg | 350 mg | 262.37 | 7.12 | 2.68
32.5-40 kg | 400 mg | 259.79 | 6.96 | 2.69
>40 kg | 600 mg | 254.78 | 6.57 | 2.82

Gender and race: The pharmacokinetics of efavirenz in patients appear to be similar between men and women and among the racial groups studied.
Renal impairment: The pharmacokinetics of efavirenz have not been studied in patients with renal insufficiency; however, less than 1% of efavirenz is excreted unchanged in the urine, so the impact of renal impairment on efavirenz elimination should be minimal.
Hepatic impairment: A multiple-dose study showed no significant effect on efavirenz pharmacokinetics in patients with mild hepatic impairment (Child-Pugh Class A) compared with controls. There were insufficient data to determine whether moderate or severe hepatic impairment (Child-Pugh Class B or C) affects efavirenz pharmacokinetics.
Drug Interaction Studies
Efavirenz has been shown in vivo to cause hepatic enzyme induction, thus increasing the biotransformation of some drugs metabolized by CYP3A and CYP2B6. In vitro studies have shown that efavirenz inhibited CYP isozymes 2C9 and 2C19 with Ki values (8.5-17 μM) in the range of observed efavirenz plasma concentrations. In in vitro studies, efavirenz did not inhibit CYP2E1 and inhibited CYP2D6 and CYP1A2 (Ki values 82-160 μM) only at concentrations well above those achieved clinically. Coadministration of efavirenz with drugs primarily metabolized by CYP2C9, CYP2C19, CYP3A, or CYP2B6 isozymes may result in altered plasma concentrations of the coadministered drug. Drugs which induce CYP3A and CYP2B6 activity would be expected to increase the clearance of efavirenz resulting in lowered plasma concentrations.
Drug interaction studies were performed with efavirenz and other drugs likely to be coadministered or drugs commonly used as probes for pharmacokinetic interaction. The effects of coadministration of efavirenz on the Cmax, AUC, and Cmin are summarized in Table 7 (effect of efavirenz on other drugs) and Table 8 (effect of other drugs on efavirenz). For information regarding clinical recommendations see Drug Interactions (7.1)

Table 7: Effect of Efavirenz on Coadministered Drug Plasma Cmax, AUC, and Cmin
Coadministered Drug | Dose | Efavirenz Dose | Number of Subjects | Coadministered Drug (mean % change)
Coadministered Drug | Dose | Efavirenz Dose | Number of Subjects | Cmax (90% CI) | AUC (90% CI) | Cmin (90% CI)
Atazanavir | 400 mg qd with a light meal d 1‑20 | 600 mg qd with a light meal d 7‑20 | 27 | ↓ 59% (49-67%) | ↓ 74% (68-78%) | ↓ 93% (90-95%)
 | 400 mg qd d 1-6, then 300 mg qd d 7-20 with ritonavir 100 mg qd and a light meal | 600 mg qd 2 h after atazanavir and ritonavir d 7-20 | 13 | ↑ 14%a (↓ 17-↑ 58%) | ↑ 39% a (2-88%) | ↑ 48% a (24-76%)
 | 300 mg qd/ritonavir 100 mg qd d 1-10 (pm), then 400 mg qd/ritonavir 100 mg qd d 11-24 (pm) (simultaneous with efavirenz) | 600 mg qd with a light snack d 11-24 (pm) | 14 | ↑ 17% (8-27%) | ↔ | ↓ 42% (31-51%)
Indinavir | 1000 mg q8h x 10 days | 600 mg qd x 10 days | 20
 | After morning dose |  |  | ↔b | ↓ 33% b (26-39%) | ↓ 39% b (24-51%)
 | After afternoon dose |  |  | ↔ b | ↓ 37% b (26-46%) | ↓ 52% b (47-57%)
 | After evening dose |  |  | ↓ 29% b (11-43%) | ↓ 46% b (37-54%) | ↓ 57% b (50-63%)
Lopinavir/ritonavir | 400/100 mg capsule q12h x 9 days | 600 mg qd x 9 days | 11,7c | ↔d | ↓ 19% d (↓ 36-↑ 3%) | ↓ 39% d (3-62%)
 | 500/125 mg tablet q12h × 10 days with efavirenz compared to 400/100 mg q12h alone | 600 mg qd × 9 days | 19 | ↑12%d (2-23%) | ↔d | ↓ 10%d (↓22-↑4%)
 | 600/150 mg tablet q12h x 10 days with efavirenz compared to 400/100 mg q12h alone | 600 mg qd x 9 days | 23 | ↑ 36% d (28-44%) | ↑ 36% d (28-44%) | ↑ 32% d (21-44%)
Nelfinavir | 750 mg q8h x 7 days | 600 mg qd x 7 days | 10 | ↑ 21% (10-33%) | ↑ 20% (8-34%) | ↔
Metabolite AG-1402 |  |  |  | ↓ 40% (30-48%) | ↓ 37% (25-48%) | ↓ 43% (21-59%)
Ritonavir | 500 mg q12h x 8 days | 600 mg qd x 10 days | 11
 | After AM dose |  |  | ↑ 24% (12-38%) | ↑ 18% (6-33%) | ↑ 42% (9-86%)e
 | After PM dose |  |  | ↔ | ↔ | ↑ 24% (3-50%) e
Saquinavir SGCf | 1200 mg q8h x 10 days | 600 mg qd x 10 days | 12 | ↓ 50% (28-66%) | ↓ 62% (45-74%) | ↓ 56% (16-77%)e
Lamivudine | 150 mg q12h x 14 days | 600 mg qd x 14 days | 9 | ↔ | ↔ | ↑ 265% (37-873%)
Tenofovirg | 300 mg qd | 600 mg qd x 14 days | 29 | ↔ | ↔ | ↔
Zidovudine | 300 mg q12h x 14 days | 600 mg qd x 14 days | 9 | ↔ | ↔ | ↑ 225% (43-640%)
Maraviroc | 100 mg bid | 600 mg qd | 12 | ↓ 51% (37-62%) | ↓ 45% (38-51%) | ↓ 45% (28-57%)
Raltegravir | 400 mg single dose | 600 mg qd | 9 | ↓ 36% (2-59%) | ↓ 36% (20-48%) | ↓ 21% (↓ 51-↑ 28%)
Boceprevir | 800 mg tid × 6 days | 600 mg qd × 16 days | NA | ↓ 8% (↓ 22-↑ 8%) | ↓ 19% (11-25%) | ↓ 44% (26-58%)
Simeprevir | 150 mg qd × 14 days | 600 mg qd × 14 days | 23 | ↓ 51% (↓ 46-↓ 56%) | ↓ 71% (↓ 67-↓ 74%) | ↓ 91% (↓ 88-↓ 92%)
Azithromycin | 600 mg single dose | 400 mg qd x 7 days | 14 | ↑ 22% (4-42%) | ↔ | NA
Clarithromycin | 500 mg q12h x 7 days | 400 mg qd x 7 days | 11 | ↓ 26% (15-35%) | ↓ 39% (30-46%) | ↓ 53% (42-63%)
14-OH metabolite |  |  |  | ↑ 49% (32-69%) | ↑ 34% (18-53%) | ↑ 26% (9-45%)
Fluconazole | 200 mg x 7 days | 400 mg qd x 7 days | 10 | ↔ | ↔ | ↔
Itraconazole | 200 mg q12h x 28 days | 600 mg x 14 days | 18 | ↓ 37% (20-51%) | ↓ 39% (21-53%) | ↓ 44% (27-58%)
Hydroxy-itraconazole |  |  |  | ↓ 35% (12-52%) | ↓ 37% (14-55%) | ↓ 43% (18-60%)
Posaconazole | 400 mg (oral suspension) bid × 10 and 20 days | 400 mg qd × 10 and 20 days | 11 | ↓ 45% (34-53%) | ↓ 50% (40-57%) | NA
Rifabutin | 300 mg qd x 14 days | 600 mg qd x 14 days | 9 | ↓ 32% (15-46%) | ↓ 38% (28-47%) | ↓ 45% (31-56%)
Voriconazole | 400 mg po q12h x 1 day, then 200 mg po q12h x 8 days | 400 mg qd x 9 days | NA | ↓ 61% h | ↓ 77% h | NA
 | 300 mg po q12h days 2‑7 | 300 mg qd x 7 days | NA | ↓ 36%i (21-49%) | ↓ 55% i (45-62%) | NA
 | 400 mg po q12h days 2‑7 | 300 mg qd x 7 days | NA | ↑ 23% i (↓ 1-↑ 53%) | ↓ 7% i (↓ 23-↑ 13%) | NA
Artemether/ lumefantrine | Artemether 20 mg/ lumefantrine 120 mg tablets (6 4-tablet doses over 3 days) | 600 mg qd × 26 days | 12
Artemether |  |  |  | ↓ 21% | ↓ 51% | NA
dihydroartemisinin |  |  |  | ↓ 38% | ↓ 46% | NA
Lumefantrine |  |  |  | ↔ | ↓ 21% | NA
Atorvastatin | 10 mg qd x 4 days | 600 mg qd x 15 days | 14 | ↓ 14% (1-26%) | ↓ 43% (34-50%) | ↓ 69% (49-81%)
Total active (including metabolites) |  |  |  | ↓ 15% (2-26%) | ↓ 32% (21-41%) | ↓ 48% (23-64%)
Pravastatin | 40 mg qd x 4 days | 600 mg qd x 15 days | 13 | ↓ 32% (↓ 59-↑ 12%) | ↓ 44% (26-57%) | ↓ 19% (0-35%)
Simvastatin | 40 mg qd x 4 days | 600 mg qd x 15 days | 14 | ↓ 72% (63-79%) | ↓ 68% (62-73%) | ↓ 45% (20-62%)
Total active (including metabolites) |  |  |  | ↓ 68% (55-78%) | ↓ 60% (52-68%) | Naj
Carbamazepine | 200 mg qd x 3 days, 200 mg bid x 3 days, then 400 mg qd x 29 days | 600 mg qd x 14 days | 12 | ↓ 20% (15-24%) | ↓ 27% (20-33%) | ↓ 35% (24-44%)
Epoxide metabolite |  |  |  | ↔ | ↔ | ↓ 13% (↓ 30-↑ 7%)
Cetirizine | 10 mg single dose | 600 mg qd x 10 days | 11 | ↓ 24% (18-30%) | ↔ | NA
Diltiazem | 240 mg x 21 days | 600 mg qd x 14 days | 13 | ↓ 60% (50-68%) | ↓ 69% (55-79%) | ↓ 63% (44-75%)
Desacetyl diltiazem |  |  |  | ↓ 64% (57-69%) | ↓ 75% (59-84%) | ↓ 62% (44-75%)
N-monodes-methyl diltiazem |  |  |  | ↓ 28% (7-44%) | ↓ 37% (17-52%) | ↓ 37% (17-52%)
Ethinyl estradiol/ Norgestimate | 0.035 mg/ 0.25 mg x 14 days | 600 mg qd x 14 days
Ethinyl estradiol |  |  | 21 | ↔ | ↔ | ↔
Norelgestromin |  |  | 21 | ↓ 46% (39-52%) | ↓ 64% (62-67%) | ↓ 82% (79-85%)
Levonorgestrel |  |  | 6 | ↓ 80% (77-83%) | ↓ 83% (79-87%) | ↓ 86% (80-90%)
Lorazepam | 2 mg single dose | 600 mg qd x 10 days | 12 | ↑ 16% (2-32%) | ↔ | NA
Methadone | Stable maintenance 35- 100 mg daily | 600 mg x 14-21 days | 11 | ↓ 45% (25-59%) | ↓ 52% (33-66%) | NA
Bupropion | 150 mg single dose (sustained-release) | 600 mg qd × 14 days | 13 | ↓ 34% (21-47%) | ↓ 55% (48-62%) | NA
Hydroxy - bupropion |  |  |  | ↓ 50% (20-80%) | ↔ | NA
Paroxetine | 20 mg qd x 14 days | 600 mg x 14 days | 16 | ↔ | ↔ | ↔
Sertraline | 50 mg qd x 14 days | 600 mg x 14 days | 13 | ↓ 29% (15-40%) | ↓ 39% (27-50%) | ↓ 46% (31-58%)
↑ Indicates increase ↓ Indicates decrease ↔ Indicates no change or a mean increase or decrease of <10%.
a Compared with atazanavir 400 mg qd alone.
b Comparator dose of indinavir was 800 mg q8h x 10 days.
c Parallel-group design; n for efavirenz + lopinavir/ritonavir, n for lopinavir/ritonavir alone.
d Values are for lopinavir; the pharmacokinetics of ritonavir in this study were unaffected by concurrent efavirenz.
e 95% CI.
f Soft Gelatin Capsule.
g Tenofovir disoproxil fumarate.
h 90% CI not available.
i Relative to steady-state administration of voriconazole (400 mg for 1 day, then 200 mg po q12h for 2 days).
j Not available because of insufficient data.
NA = not available.

Table 8: Effect of Coadministered Drug on Efavirenz Plasma Cmax, AUC, and Cmin
 |  |  |  | Efavirenz (mean % change)
Coadministered Drug | Dose | Efavirenz Dose | Number of Subjects | C max (90% CI) | AUC (90% CI) | C min (90% CI)
Indinavir | 800 mg q8h x 14 days | 200 mg qd x 14 days | 11 | ↔ | ↔ | ↔
Lopinavir/ ritonavir | 400/100 mg q12h x 9 days | 600 mg qd x 9 days | 11,12a | ↔ | ↓ 16% (↓ 38-↑ 15%) | ↓ 16% (↓ 42-↑ 20%)
Nelfinavir | 750 mg q8h x 7 days | 600 mg qd x 7 days | 10 | ↓ 12% (↓ 32-↑ 13%)b | ↓ 12% (↓ 35-↑ 18%)b | ↓ 21% (↓ 53-↑ 33%)
Ritonavir | 500 mg q12h x 8 days | 600 mg qd x 10 days | 9 | ↑ 14% (4-26%) | ↑ 21% (10-34%) | ↑ 25% (7-46%)b
Saquinavir SGCc | 1200 mg q8h x 10 days | 600 mg qd x 10 days | 13 | ↓ 13% (5-20%) | ↓ 12% (4-19%) | ↓ 14% (2-24%)b
Tenofovird | 300 mg qd | 600 mg qd x 14 days | 30 | ↔ | ↔ | ↔
Boceprevir | 800 mg tid x 6 days | 600 mg qd x 16 days | NA | ↑ 11% (2-20%) | ↓ 20% (15-26%) | NA
Simeprevir | 150 mg qd x 14 days | 600 mg qd x 14 days | 23 | ↔ | ↓ 10% (5-15%) | ↓ 13% (7-19%)
Azithromycin | 600 mg single dose | 400 mg qd x 7 days | 14 | ↔ | ↔ | ↔
Clarithromycin | 500 mg q12h x 7 days | 400 mg qd x 7 days | 12 | ↑ 11% (3-19%) | ↔ | ↔
Fluconazole | 200 mg x 7 days | 400 mg qdx 7 days | 10 | ↔ | ↑ 16% (6-26%) | ↑ 22% (5-41%)
Itraconazole | 200 mg q12h x 14 days | 600 mg qdx 28 days | 16 | ↔ | ↔ | ↔
Rifabutin | 300 mg qd x 14 days | 600 mg qdx 14 days | 11 | ↔ | ↔ | ↓ 12% (↓ 24-↑ 1%)
Rifampin | 600 mg x 7 days | 600 mg qd x 7 days | 12 | ↓ 20% (11-28%) | ↓ 26% (15-36%) | ↓ 32% (15-46%)
Voriconazole | 400 mg po q12h x 1 day, then 200 mg po q12h x 8 days | 400 mg qd x 9 days | NA | ↑ 38%e | ↑ 44%e | NA
 | 300 mg po q12h days 2-7 | 300 mg qd x 7 days | NA | ↓ 14%f (7-21%) | ↔f | NA
 | 400 mg po q12h days 2-7 | 300 mg qd x 7 days | NA | ↔f | ↑ 17%f (6-29%) | NA
Artemether/Lumefantrine | Aremether 20 mg/lumefantrine 120 mg tablets (64-tablets doses over 3 days) | 600 mg qd x 26 days | 12 | ↔ | ↓ 17% | NA
Atorvastatin | 10 mg qd x 4 days | 600 mg qd x 15 days | 14 | ↔ | ↔ | ↔
Pravastatin | 40 mg qd x 4 days | 600 mg qd x 15 days | 11 | ↔ | ↔ | ↔
Simvastatin | 40 mg qd x 4 days | 600 mg qd x 15 days | 14 | ↓ 12% (↓ 28-↑ 8%) | ↔ | ↓ 12% (↓ 25-↑ 3%)
Aluminum hydroxide 400 mg, magnesium hydroxide 400 mg, plus simethicone 40 mg | 30 mL single dose | 400 mg single dose | 17 | ↔ | ↔ | NA
Carbamazepine | 200 mg qd x 3 days, 200 mg bid x 3 days, then 400 mg qd x 15 days | 600 mg qd x 35 days | 14 | ↓21% (15-26%) | ↓36% (32-40%) | ↓47% (41-53%)
Cetirizine | 10 mg single dose | 600 mg qd x 10 days | 11 | ↔ | ↔ | ↔
Diltiazem | 240 mg x 14 days | 600 mg qd x 28 days | 12 | ↑ 16% (6-26%) | ↑ 11% (5-18%) | ↑ 13% (1-26%)
Famotidine | 40 mg single dose | 400 mg single dose | 17 | ↔ | ↔ | NA
Paroxetine | 20 mg qd x 14 days | 600 mg qd x 14 days | 12 | ↔ | ↔ | ↔
Sertraline | 50 mg qd x 14 days | 600 mg qd x 14 days | 13 | ↑ 11% (6-16%) | ↔ | ↔
↑ Indicates increase ↓ Indicates decrease ↔ Indicates no change or a mean increase or decrease of <10%.
a Parallel-group design; n for efavirenz + lopinavir/ritonavir, n for efavirenz alone.
b 95% CI.
c Soft Gelatin Capsule.
d Tenofovir disoproxil fumarate.
e 90% CI not available.
f Relative to steady-state administration of efavirenz (600 mg once daily for 9 days).
NA = not available.

12.4 Microbiology

Mechanism of Action
Efavirenz is an NNRTI of HIV-1. Efavirenz activity is mediated predominantly by noncompetitive inhibition of HIV-1 reverse transcriptase. HIV-2 reverse transcriptase and human cellular DNA polymerases α,β, γ, and δ are not inhibited by efavirenz.
Antiviral Activity in Cell Culture
The concentration of efavirenz inhibiting replication of wild-type laboratory adapted strains and clinical isolates in cell culture by 90-95% (EC90-95) ranged from 1.7 to 25 nM in lymphoblastoid cell lines, peripheral blood mononuclear cells (PBMCs), and macrophage/monocyte cultures. Efavirenz demonstrated antiviral activity against clade B and most non-clade B isolates (subtypes A, AE, AG, C, D, F, G, J, N), but had reduced antiviral activity against group O viruses. Efavirenz demonstrated additive antiviral activity without cytotoxicity against HIV-1 in cell culture when combined with the NNRTIs delavirdine (DLV) and nevirapine (NVP), NRTIs (abacavir, didanosine, emtricitabine, lamivudine [LAM], stavudine, tenofovir, zalcitabine, zidovudine [ZDV]), PIs (amprenavir, indinavir [IDV], lopinavir, nelfinavir, ritonavir, saquinavir), and the fusion inhibitor enfuvirtide. Efavirenz demonstrated additive to antagonistic antiviral activity in cell culture with atazanavir. Efavirenz was not antagonistic with adefovir, used for the treatment of hepatitis B virus infection, or ribavirin, used in combination with interferon for the treatment of hepatitis C virus infection.
Resistance
In cell culture
In cell culture, HIV-1 isolates with reduced susceptibility to efavirenz (>380-fold increase in EC90 value) emerged rapidly in the presence of drug. Genotypic characterization of these viruses identified single amino acid substitutions L100I or V179D, double substitutions L100I/V108I, and triple substitutions L100I/V179D/Y181C in reverse transcriptase.
Clinical studies
Clinical isolates with reduced susceptibility in cell culture to efavirenz have been obtained. One or more substitutions at amino acid positions 98, 100, 101, 103, 106, 108, 188, 190, 225, and 227 in reverse transcriptase were observed in patients failing treatment with efavirenz in combination with indinavir, or with zidovudine plus. The K103N substitution was the most frequently observed. Long-term resistance surveillance (average 52 weeks, range 4-106 weeks) analyzed 28 matching baseline and virologic failure isolates. Sixty-one percent (17/28) of these failure isolates had decreased efavirenz susceptibility in cell culture with a median 88-fold change in efavirenz susceptibility (EC50 value) from reference. The most frequent NNRTI substitution to develop in these patient isolates was K103N (54%). Other NNRTI substitutions that developed included L100I (7%), K101E/Q/R (14%), V108I (11%), G190S/T/A (7%), P225H (18%), and M230I/L (11%).
Cross-Resistance
Cross-resistance among NNRTIs has been observed. Clinical isolates previously characterized as efavirenz -resistant were also phenotypically resistant in cell culture to delavirdine and nevirapine compared to baseline. Delavirdine-and/or nevirapine-resistant clinical viral isolates with NNRTI resistance-associated substitutions (A98G, L100I, K101E/P, K103N/S, V106A, Y181X, Y188X, G190X, P225H, F227L, or M230L) showed reduced susceptibility to efavirenz in cell culture. Greater than 90% of NRTI-resistant clinical isolates tested in cell culture retained susceptibility to efavirenz.

13 NONCLINICAL TOXICOLOGY

13.1 Carcinogenesis & Mutagenesis & Impairment Of Fertility

Carcinogenesis
Long-term carcinogenicity studies in mice and rats were carried out with efavirenz. Mice were dosed with 0, 25, 75, 150, or 300 mg/kg/day for 2 years. Incidences of hepatocellular adenomas and carcinomas and pulmonary alveolar/bronchiolar adenomas were increased above background in females. No increases in tumor incidence above background were seen in males. There was no NOAEL in females established for this study because tumor findings occurred at all doses. AUC at the NOAEL (150 mg/kg) in the males was approximately 0.9 times that in humans at the recommended clinical dose. In the rat study, no increases in tumor incidence were observed at doses up to 100 mg/kg/day, for which AUCs were 0.1 (males) or 0.2 (females) times those in humans at the recommended clinical dose.
Mutagenesis
Efavirenz tested negative in a battery of in vitro and in vivo genotoxicity assays. These included bacterial mutation assays in S. typhimurium and E. coli, mammalian mutation assays in Chinese hamster ovary cells, chromosome aberration assays in human peripheral blood lymphocytes or Chinese hamster ovary cells, and an in vivo mouse bone marrow micronucleus assay.
Impairment of Fertility
Efavirenz did not impair mating or fertility of male or female rats, and did not affect sperm of treated male rats. The reproductive performance of offspring born to female rats given efavirenz was not affected. The AUCs at the NOAEL values in male (200 mg/kg) and female (100 mg/kg) rats were approximately ≤0.15 times that in humans at the recommended clinical dose.

13.2 Animal Toxicology

Nonsustained convulsions were observed in 6 of 20 monkeys receiving efavirenz at doses yielding plasma AUC values 4- to 13-fold greater than those in humans given the recommended dose [see Warnings and Precautions (5.10)].

14 CLINICAL STUDIES

14.1 Adults

Study 006, a randomized, open-label trial, compared efavirenz tablets (600 mg once daily) + zidovudine (ZDV, 300 mg q12h) + lamivudine (LAM, 150 mg q12h) or efavirenz tablets(600 mg once daily) + indinavir (IDV, 1000 mg q8h) with indinavir (800 mg q8h) + zidovudine (300 mg q12h) + lamivudine (150 mg q12h). Twelve hundred sixty-six patients (mean age 36.5 years [range 18-81], 60% Caucasian, 83% male) were enrolled. All patients were efavirenz-, lamivudine-, NNRTI-, and PI-naive at study entry. The median baseline CD4+ cell count was 320 cells/mm3 and the median baseline HIV-1 RNA level was 4.8 log10 copies/mL. Treatment outcomes with standard assay (assay limit 400 copies/mL) through 48 and 168 weeks are shown in Table 9
Plasma HIV RNA levels were quantified with standard (assay limit 400 copies/mL) and ultrasensitive (assay limit 50 copies/mL) versions of the AMPLICOR HIV-1 MONITOR assay. During the study, version 1.5 of the assay was introduced in Europe to enhance detection of non-clade B virus.

Table 9: Outcomes of Randomized Treatment Through 48 and 168 Weeks, Study 006
 | EFAVIRENZ+ ZDV + LAM n=422 |  | EFAVIRENZ+ IDV n=429 |  | IDV + ZDV + LAM n=415
Outcome | Week 48 | Week 168 | Week 48 | Week 168 | Week 48 | Week 168
Respondera | 69% | 48% | 57% | 40% | 50% | 29%
Virologic failureb | 6% | 12% | 15% | 20% | 13% | 19%
Discontinued for adverse events | 7% | 8% | 6% | 8% | 16% | 20%
Discontinued for other reasonsc | 17% | 31% | 22% | 32% | 21% | 32%
CD4+ cell count (cells/mm^3)
Observed subjects (n) | (279) | (205) | (256) | (158) | (228) | (129)
Mean change from baseline | 190 | 329 | 191 | 319 | 180
a Patients achieved and maintained confirmed HIV-1 RNA <400 copies/mL through Week 48 or Week 168.
b Includes patients who rebounded, patients who were on study at Week 48 and failed to achieve confirmed HIV-1 RNA <400 copies/mL at time of discontinuation, and patients who discontinued due to lack of efficacy.
c Includes consent withdrawn, lost to follow-up, noncompliance, never treated, missing data, protocol violation, death, and other reasons. Patients with HIV-1 RNA levels<400 copies/mL who chose not to continue in the voluntary extension phases of the study were censored at date of last dose of study medication.

For patients treated with efavirenz+ zidovudine + lamivudine, efavirenz+ indinavir, or indinavir + zidovudine + lamivudine, the percentage of responders with HIV-1 RNA <50 copies/mL was 65%, 50%, and 45%, respectively, through 48 weeks, and 43%, 31%, and 23%, respectively, through 168 weeks. A Kaplan-Meier analysis of time to loss of virologic response (HIV RNA <400 copies/mL) suggests that both the trends of virologic response and differences in response continue through 4 years.

ACTG 364 is a randomized, double-blind, placebo-controlled, 48-week study in NRTI-experienced patients who had completed two prior ACTG studies. One-hundred ninety-six patients (mean age 41 years [range 18-76], 74% Caucasian, 88% male) received NRTIs in combination with efavirenz (600 mg once daily), or nelfinavir (NFV, 750 mg three times daily), or efavirenz (600 mg once daily) + nelfinavir in a randomized, double-blinded manner. The mean baseline CD4+ cell count was 389 cells/mm 3 and mean baseline HIV-1 RNA level was 8130 copies/mL. Upon entry into the study, all patients were assigned a new open-label NRTI regimen, which was dependent on their previous NRTI treatment experience. There was no significant difference in the mean CD4+ cell count among treatment groups; the overall mean increase was approximately 100 cells at 48 weeks among patients who continued on study regimens. Treatment outcomes are shown in Table 11. Plasma HIV RNA levels were quantified with the AMPLICOR HIV-1 MONITOR assay using a lower limit of quantification of 500 copies/mL.

Table 10: Outcomes of Randomized Treatment Through 48 Weeks, Study ACTG 364*
Outcome | EFAVIRENZ+ NFV + NRTIs n=65 | EFAVIRENZ+ NRTIs n=65 | NFV + NRTIs n=66
HIV-1 RNA <500 copies/mLa | 71% | 63% | 41%
HIV-1 RNA ≥500 copies/mLb | 17% | 34% | 54%
CDC Category C Event | 2% | 0% | 0%
Discontinuations for adverse eventsc | 3% | 3% | 5%
Discontinuations for other reasonsd | 8% | 0% | 0%
* For some patients, Week 56 data were used to confirm the status at Week 48.
a Subjects achieved virologic response (two consecutive viral loads <500 copies/mL) and maintained it through Week 48.
b Includes viral rebound and failure to achieve confirmed <500 copies/mL by Week 48.
c See Adverse Reactions (6.1) for a safety profile of these regimens.
d Includes loss to follow-up, consent withdrawn, noncompliance.

A Kaplan-Meier analysis of time to treatment failure through 72 weeks demonstrates a longer duration of virologic suppression (HIV RNA <500 copies/mL) in the efavirenz-containing treatment arms.

14.2 Pediatric Patients

Study AI266922 is an open-label study to evaluate the pharmacokinetics, safety, tolerability, and antiviral activity of efavirenz in combination with didanosine and emtricitabine in antiretroviral-naive and -experienced pediatric patients. Thirty-seven patients 3 months to 6 years of age (median 0.7 years) were treated with efavirenz. At baseline, median plasma HIV-1 RNA was 5.88 log10 copies/mL, median CD4+ cell count was 1144 cells/mm^3, and median CD4+ percentage was 25%. The median time on study therapy was 60 weeks; 27% of patients discontinued before Week 48. Using an ITT analysis, the overall proportions of patients with HIV RNA <400 copies/mL and <50 copies/mL at Week 48 were 57% (21/37) and 46% (17/37), respectively. The median increase from baseline in CD4+ count at 48 weeks was 196 cells/mm3 and the median increase in CD4+ percentage was 6%.
Study PACTG 1021 was an open-label study to evaluate the pharmacokinetics, safety, tolerability, and antiviral activity of efavirenz in combination with didanosine and emtricitabine in pediatric patients who were antiretroviral therapy naive. Forty-three patients 3 months to 21 years of age (median 9.6 years) were dosed with efavirenz. At baseline, median plasma HIV-1 RNA was 4.8 log10 copies/mL, median CD4+ cell count was 367 cells/mm^3, and median CD4+ percentage was 18%. The median time on study therapy was 181 weeks; 16% of patients discontinued before Week 48. Using an ITT analysis, the overall proportions of patients with HIV RNA <400 copies/mL and <50 copies/mL at Week 48 were 77% (33/43) and 70% (30/43),respectively. The median increase from baseline in CD4+ count at 48 weeks of therapy was 238 cells/mm3 and the median increase in CD4+ percentage was 13%.
Study PACTG 382 was an open-label study to evaluate the pharmacokinetics, safety, tolerability, and antiviral activity of efavirenz in combination with nelfinavir and an NRTI in antiretroviralnaive and NRTI-experienced pediatric patients. One hundred two patients 3 months to 16 years of age (median 5.7 years) were treated with efavirenz. Eighty-seven percent of patients had received prior antiretroviral therapy. At baseline, median plasma HIV-1 RNA was4.57 log10 copies/mL, median CD4+ cell count was 755 cells/mm^3, and median CD4+ percentage was 30%. The median time on study therapy was 118 weeks; 25% of patients discontinued before Week 48. Using an ITT analysis, the overall proportion of patients with HIV RNA <400 copies/mL and <50 copies/mL at Week 48 were 57% (58/102) and 43% (44/102), respectively. The median increase from baseline in CD4+ count at 48 weeks of therapy was 128 cells/mm3 and the median increase in CD4+ percentage was 5%.

16 HOW SUPPLIED/STORAGE AND HANDLING

16.2 Tablets

Efavirenz tablets, USP are available as follows:
Tablets 600 mg are yellow, biconvex, capsule-shaped, film-coated tablets, engraved with "ML 12" on one side and plain on the other side.
Bottles of 30 NDC 33342-013-07

16.3 Storage

Efavirenz tablets should be stored at 20° to 25°C (68° to 77°F); excursions permitted to 15° to 30°C (59° to 86°F) [See USPControlled Room Temperature].

17 PATIENT COUNSELING INFORMATION

Advise the patient to read the FDA-approved patient labeling (Patient Information and Instructions for Use).
Drug Interactions
A statement to patients and healthcare providers is included on the product's bottle labels: ALERT: Find out about medicines that should NOT be taken with efavirenz tablets.
Efavirenz tablets may interact with some drugs; therefore, advise patients to report to their doctor the use of any other prescription, nonprescription medication.
General Information for Patients
Infom patients that efavirenz tablets is not a cure for HIV-1 infection and patients may continue to experience illnesses associated with HIV-1 infection, including opportunistic infections. Patients should remain under the care of a physician while taking efavirenz tablets.
Advised patients to avoid doing things that can spread HIV-1 infection to others.
Do not share or reuse needles or other injection equipment.
Do not share personal items that can have blood or body fluids on them, like toothbrushes and razor blades.
Do not have any kind of sex without protection. Always practice safer sex by using a latex or polyurethane condom to lower the chance of sexual contact with semen, vaginal secretions, or blood.
Do not breastfeed. Mothers with HIV-1 should not breastfeed because HIV-1 can be passed to the baby in breast milk.
Dosing Instructions
Advised patients to take efavirenz tablets. every day as prescribed. If a patient forgets to take efavirenz tablets, tell the patient to take the missed dose right away, unless it is almost time for the next dose. Advise the patient not to take 2 doses at one time and to take the next dose at the regularly scheduled time. Advise the patient to ask a healthcare provider if he/she needs help in planning the best times to take his/her medicine.
Efavirenz tablets must always be used in combination with other antiretroviral drugs. Advised patients to take efavirenz tablets on an empty stomach, preferably at bedtime. Taking efavirenz tablets with food increases efavirenz concentrations and may increase the frequency of adverse reactions. Dosing at bedtime may improve the tolerability of nervous system symptoms [see Dosage and Administration (2) and Adverse Reactions (6.1)]. Healthcare providers should assist parents or caregivers in determining the best efavirenz tablets. dosing schedule for infants and young children.
For adult and pediatric patients who cannot swallow capsules or tablets, patients or their caregivers should be advised to read and carefully follow the instructions for administering the capsule contents in a small amount of food or infant formula [see Dosage and Administration (2.3) and FDA-approved patient labeling (Patient Information and Instructions for Use)]. Patients should call their healthcare provider or pharmacist if they have any questions.
Nervous System Symptoms
Inform patients that central nervous system symptoms (NSS) including dizziness, insomnia, impaired concentration, drowsiness, and abnormal dreams are commonly reported during the first weeks of therapy with efavirenz tablets [see Warnings and Precautions (5.6)]. Dosing at bedtime may improve the tolerability of these symptoms, which are likely to improve with continued therapy. Patients should be alerted to the potential for additive effects when efavirenz tablets is used concomitantly with alcohol or psychoactive drugs. Alert patients that if they experience NSS they should avoid potentially hazardous tasks such as driving or operating machinery.
Inform patients that there is a risk of developing late-onset neurotoxicity, including ataxia and encephalopathy which may occur months to years after beginning efavirenz tablets therapy [see Warnings and Precautions (5.6)].
Psychiatric Symptoms
Inform patients that serious psychiatric symptoms including severe depression, suicide attempts, aggressive behavior, delusions, paranoia, psychosis-like symptoms and catatonia have been reported in patients receiving efavirenz tablets [see Warnings and Precautions (5.5)]. If they experience severe psychiatric adverse experiences they should seek immediate medical evaluation. Advise patients to inform their physician of any history of mental illness or substance abuse.

Rash
Inform patients that a common side effect is rash [see Warnings and Precautions (5.8)]. Rashes usually go away without any change in treatment. However, since rash may be serious, advise patients to contact their physician promptly if rash occurs.
Hepatotoxicity
Inform patients to watch for early warning signs of liver inflammation or failure, such as fatigue, weakness, lack of appetite, nausea and vomiting, as well as later signs such as jaundice, confusion, abdominal swelling, and discolored feces, and to consult their health care professional without delay if such symptoms occur [see Warnings and Precautions (5.9) and Adverse Reactions (6.1)].
Females of Reproductive Potential
Advise females of reproductive potential to use effective contraception as well as a barrier method during treatment with efavirenz tablets and for 12 weeks after discontinuing efavirenz tablets . Advise patients to contact their healthcare provider if they plan to become pregnant, become pregnant, or if pregnancy is suspected during treatment with efavirenz tablets [see Warnings and Precautions (5.7) and Use in Specific Populations (8.1, 8.3)].
Pregnancy Exposure Registry
Advise patients that there is a pregnancy exposure registry that monitors pregnancy outcomes in women exposed to efavirenz tablets during pregnancy [see Use in Specific Populations (8.1)].
Fat Redistribution
Inform patients that redistribution or accumulation of body fat may occur in patients receiving antiretroviral therapy and that the cause and long-term health effects of these conditions are not known [see Warnings and Precautions (5.13)].

The brands listed herein are trademarks of their respective owners.

Manufactured for :
Macleods Pharma USA, Inc.

Princeton, NJ 08540

Manufactured by:
Macleods Pharmaceuticals Ltd.
Baddi, Himachal Pradesh, INDIA
Revised: 06/2024

.

SPL PATIENT PACKAGE INSERT SECTION

Patient Information
Efavirenz tablets
(eh-FAH-vih-rehnz)
Important: Ask your doctor or pharmacist about medicines that should not be taken with efavirenz tablets. For more information, see the section "What should I tell my doctor before taking efavirenz tablets?"
Read this Patient Information before you start taking efavirenz

tablets and each time you get a refill. There may be new information. This information does not take the place of talking with your doctor about your medical condition or treatment.
What is efavirenz tablets?
Efavirenz tablets is a prescription HIV-1 (Human Immunodeficiency Virus type 1) medicine used with other antiretroviral medicines to treat HIV-1 infection in adults and in children who are at least 3 months old and who weigh at least 7 pounds 12 ounces(3.5 kg). HIV is the virus that causes AIDS (Acquired Immune Deficiency Syndrome).
It is not known if efavirenz tablets is safe and effective in children younger than 3 months of age or who weigh less than 7 pounds 12 ounces (3.5 kg).
When used with other antiretroviral medicines to treat HIV-1 infection, efavirenz tablets may help:
•reduce the amount of HIV-1 in your blood. This is called viral load.
•increase the number of CD4+ (T) cells in your blood that help fight off otherinfections.
Reducing the amount of HIV-1 and increasing the CD4+ (T) cells in your blood may help improve your immune system. This may reduce your risk of death or getting infections that can happen when your immune system is weak (opportunistic infections).
Efavirenz does not cure HIV-1 infection or AIDS. You should keep taking HIV-1 medicines to control HIV-1 infection and decrease HIV-related illnesses.
Avoid doing things that can spread HIV-1 infection to others:
•Do not share or reuse needles or other injection equipment.
•Do not share personal items that can have blood or body fluids on them, like toothbrushes and razor blades.
•Do not have any kind of sex without protection. Always practice safer sex by using a latex or polyurethane condom to lower the chance of sexual contact with any body fluids such as semen, vaginal secretions, or blood.
Ask your doctor if you have any questions about how to prevent passing HIV to other people.
Who should not take efavirenz tablets?
Do not take efavirenz tablets if you are allergic to efavirenz or any of the ingredients in efavirenz tablets. See the end of this leaflet for a complete list of ingredients in efavirenz tablets.
Do not take efavirenz tablets if you are currently taking elbasvir and grazoprevir (ZEPATIER ®).
What should I tell my doctor before taking Efavirenz tablets?
Before taking efavirenz tablets, tell your doctor if you have any medical conditions and in particular, if you:
•have a heart condition
•have ever had a mental health problem
•have ever used street drugs or large amounts of alcohol
•have liver problems, including hepatitis B or C virus infection
•have a history of seizures
•are pregnant or plan to become pregnant. Efavirenz tablets may harm your unborn baby. If you are able to become pregnant your healthcare provider should do a pregnancy test before you start efavirenz. You should not become pregnant while taking efavirenz and for 12 weeks after stopping treatment with efavirenz tablets.
Females who are able to become pregnant should use 2 effective forms of birth control during treatment and for 12 weeks after stopping treatment with efavirenz tablets. A barrier form of birth control should always be used along with another type of birth control.
•Barrier forms of birth control may include latex or polyurethane condom, contraceptive sponge, diaphragm with spermicide, and cervical cap.
•Hormonal forms of birth control, such as birth control pills, injections, vaginal rings, or implants may not work during treatment with efavirenz tablets.
•Talk to your doctor about forms of birth control that may be used during treatment with efavirenz tablets.
•Pregnancy Registry. There is a pregnancy registry for women who take antiretroviral medicines during pregnancy. The purpose of this registry is to collect information about the health of you and your baby. Talk to your doctor about how you can take part in this registry.
•Do not breastfeed if you take efavirenz tablets.
•You should not breastfeed if you have HIV because of the risk of passing HIV to your baby.
Tell your doctor and pharmacist about all the medicines you take, including prescription and over-the-counter medicines, vitamins, and herbal supplements.
Efavirenz tabletsmay affect the way other medicines work, and other medicines may affect how efavirenz works, and may cause serious side effects. If you take certain medicines with efavirenz, the amount of efavirenz in your body may be too low and it may not work to help control your HIV infection. The HIV virus in your body may become resistant to efavirenz or other HIV medicines that are like it.
You should not take efavirenz tablets if you take ATRIPLA (efavirenz, emtricitabine, tenofovir disoproxil fumarate) unless your doctor tells you to.
Tell your doctor and pharmacist about all the medicines you take, including prescription and over-the-counter medicines, vitamins, and herbal supplements. Some medicines interact with efavirenz.
Keep a list of your medicines to show your doctor and pharmacist.
•You can ask your doctor or pharmacist for a list of medicines that interact with efavirenz.
•Do not start taking a new medicine without telling your doctor. Your doctor can tell you if it is safe to take efavirenz with other medicines.
How should I take efavirenz tablets?
•Take efavirenz exactly as your doctor tells you to.
•Do not change your dose or stop taking efavirenz unless your doctor tells you to.
•Stay under the care of your doctor during treatment with efavirenz.
•Efavirenz must be used with other antiretroviral medicines.
•Take efavirenz tablets 1 time each day.
•Efavirenz tablets comes as tablets.
•Efavirenz tablets must not be broken.
•Swallow efavirenz tablets whole with liquid.
How and when to take efavirenz tablets.
•You should take efavirenz tablets on an empty stomach at bedtime. Taking efavirenz tablets with food increases the amount of medicine in your body. Some side effects may bother you less if you take Efavirenz on an empty stomach and at bedtime.
•Your child's doctor will prescribe the right dose of Efavirenz based on your child's weight.
•If you have difficulty swallowing tablets, tell your doctor..
•Do not miss a dose of efavirenz. If you forget to take efavirenz, take the missed dose right away, unless it is almost time for your next dose. Do not take 2 doses at one time. Just take your next dose at your regularly scheduled time. If you need help in planning the best times to take your medicine, ask your doctor or pharmacist.
•If you take too much efavirenz, call your doctor or go to the nearest hospital emergency room right away.
•When your efavirenz supply starts to run low, get more from your doctor or pharmacy. It is important not to run out of efavirenz. The amount of HIV-1 in your blood may increase if the medicine is stopped for even a short time. The virus may become resistant to efavirenz and harder to treat.
What are the possible side effects of efavirenz?
Efavirenz tablets may cause serious side effects, including:
• Serious mental health problems can happen in people who take efavirenz. Tell your doctor right away if you have any of the following symptoms:
• feel sad or hopeless • do not trust other people
• feel anxious or restless • hear or see things that are not
• are not able to move or speak normally
• have thoughts of hurting yourself (suicide) or have tried to hurt yourself or others
• Are not able to tell the difference between what is true or real and what is false or unreal
• Nervous system symptoms are common in people who take efavirenz and can be severe. These symptoms usually begin during the first or second day of treatment with efavirenz and usually go away after 2 to 4 weeks of treatment.
Some symptoms may occur months to years after beginning efavirenz tablets therapy.
These symptoms may become worse if you drink alcohol, take a medicine for mental health problems, or use certain street drugs during treatment with efavirenz. Symptoms may include:
• dizziness • trouble sleeping
• trouble concentrating • unusual dreams
• drowsiness • lack of coordination or difficulty with balance
If you have dizziness, trouble concentrating or drowsiness, do not drive a car, use machinery, or do anything that needs you to be alert.
Some nervous system symptoms (e.g. confusion, slow thoughts and physical movement, and delusions [false beliefs] or hallucinations [seeing or hearing things that others do not see or hear]) may occur months to years after beginning efavirenz tablets therapy. Promptly contact your health care provider should any of these symptoms occur.
• Skin rash is common with efavirenz but can sometimes be severe. Skin rash usually goes away without any change in treatment. If you develop a rash with any of the following symptoms, tell your doctor right away:
• skin rash,with or without itching • peeling skin
• fever • mouth sores
• swelling of your face • red or inflamed eyes, like “pink eye (conjunctivitis)
• blisters or skin lesions
•Liver problems, including liver failure and death can happen in people who take efavirenz. Liver problems can happen in people without a history of liver problems. Your doctor will do blood tests to check your liver before you start efavirenz and during treatment. Tell your doctor right away if you get any of the following symptoms:
• your skin or the white part of your eyes turns yellow (jaundice) •you don't feel like eating food for several days or longer
• your urine turns dark • you feel sick to your stomach (nausea)
• your bowel movements (stools) turn light in color • you have lower stomach area (abdominal) pain
•Seizures can happen in people who take efavirenz. Seizures are more likely to happen if you have had seizures in the past. Tell your doctor if you have had a seizure or if you take a medicine to help prevent seizures.
•Changes in your immune system (Immune Reconstitution Syndrome) can happen when you start taking HIV-1 medicines. Your immune system may get stronger and begin to fight infections that have been hidden in your body for a long time. Tell your doctor if you start having new symptoms after starting your HIV-1 medicine.
•Changes in body fat can happen in people who take HIV-1 medicine. These changes may include increased amount of fat in the upper back and neck (“buffalo hump”), breast, and around the main part of your body (trunk). Loss of fat from the legs, arms, and face may also happen. The cause and long-term health effects of these conditions are not known.
The most common side effects of efavirenz tablets include:
• rash • abnormal dreams
• dizziness • tiredness
• nausea • trouble sleeping
• headache • vomiting
• difficulty concentrating
Some patients taking efavirenz have experienced increased levels of lipids (cholesterol and triglycerides) in the blood. Tell your doctor if you have any side effect that bothers you or that does not go away.
These are not all the possible side effects of efavirenz. For more information, ask your doctor or pharmacist.
Call your doctor for medical advice about side effects. You may report side effects to FDA at 1-800-FDA-1088.
How should I store efavirenz tablets?
• Store efavirenz tablets at room temperature between 68°F to 77°F (20°C to 25°C).
Keep efavirenz tablets and all medicines out of the reach of children.
General information about efavirenz tablets
Medicines are sometimes prescribed for purposes other than those listed in a Patient Information leaflet. Do not use efavirenz for a condition for which it was not prescribed. Do not give efavirenz to other people, even if they have the same symptoms that you have. It may harm them.
If you would like more information, talk with your doctor. You can ask your pharmacist or doctor for information about efavirenz that is written for health professionals. For more information, call Macleods Pharmaceutical Ltd at 1-314-814-2833.
What are the ingredients in efavirenz tablets?
Active ingredient: efavirenz
Inactive ingredients:
Efavirenz tablets: croscarmellose sodium, hydroxypropyl cellulose, lactose monohydrate, magnesium stearate, microcrystalline cellulose, and sodium lauryl sulfate. The film coating contains Opadry Yellow,consisting of hydroxypropylmethyl cellulose, titanium dioxide, polyethylene glycol and iron oxide yellow.
This Patient Information has been approved by the U.S. Food and Drug Administration.
Manufactured for :
Macleods Pharma USA, Inc.

Princeton, NJ 08540

Manufactured by:
Macleods Pharmaceuticals Ltd.
Baddi, Himachal Pradesh, INDIA
The brands listed herein are trademarks of their respective owners.
Revised: May 2024

PACKAGE LABEL.PRINCIPAL DISPLAY PANEL

Efavirenz Tablets , USP 600 mg
NDC 33342-013-07
30's container